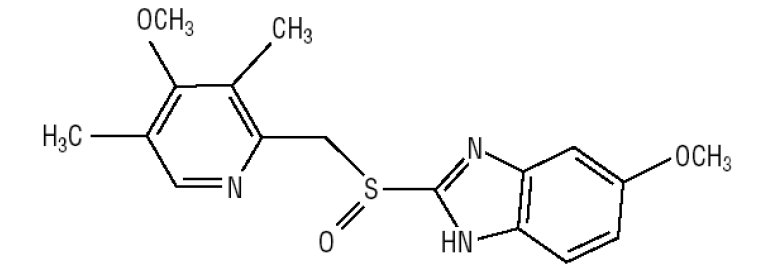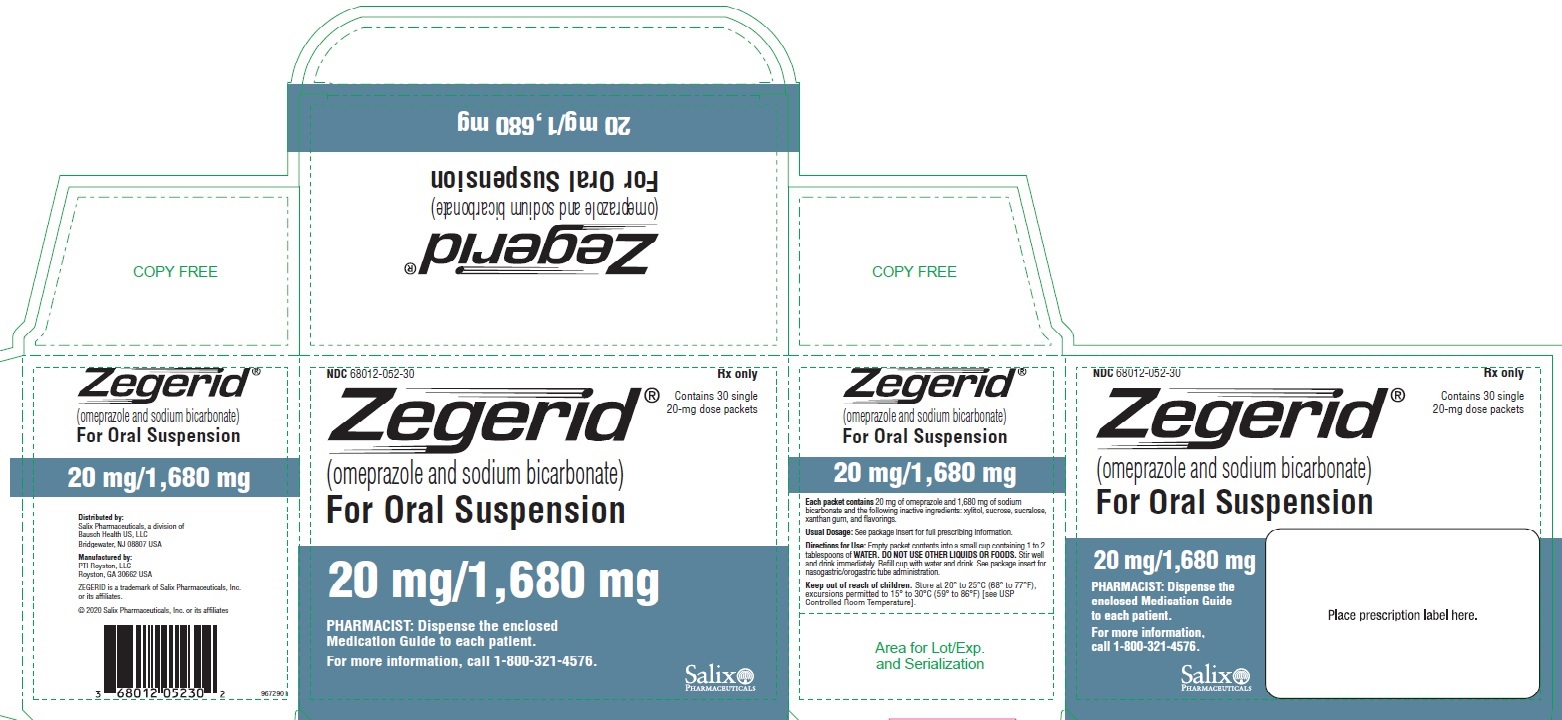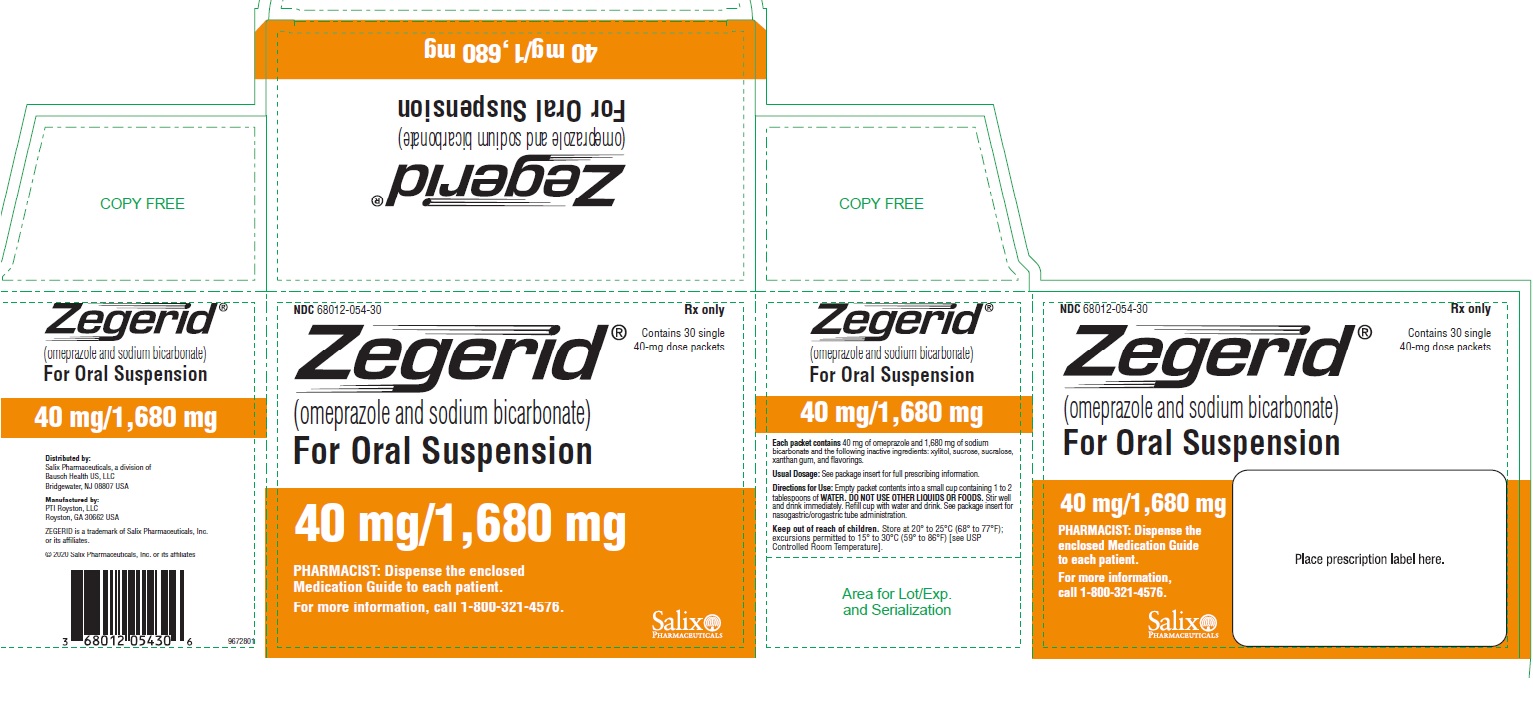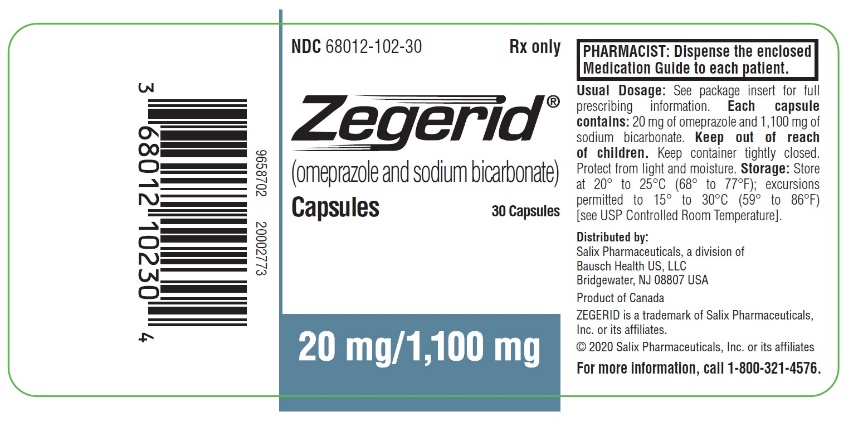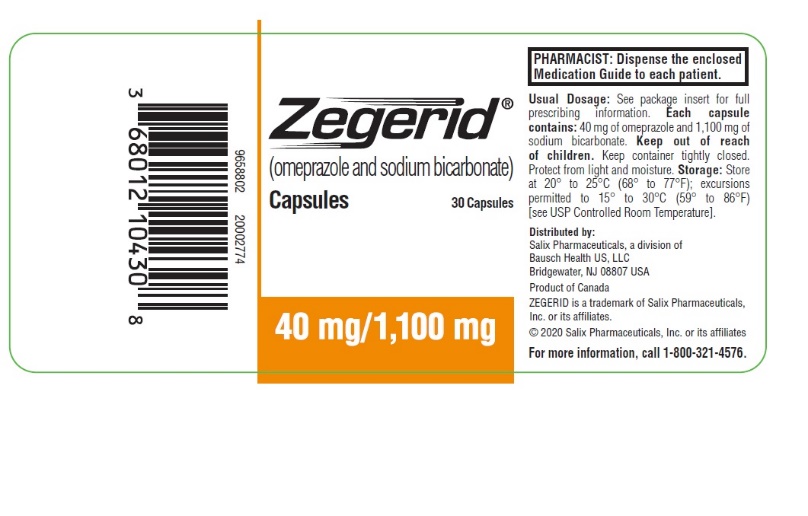 DRUG LABEL: ZEGERID
NDC: 68012-052 | Form: POWDER, FOR SUSPENSION
Manufacturer: Santarus, Inc..
Category: prescription | Type: HUMAN PRESCRIPTION DRUG LABEL
Date: 20230719

ACTIVE INGREDIENTS: OMEPRAZOLE 20 mg/1 1; SODIUM BICARBONATE 1680 mg/1 1
INACTIVE INGREDIENTS: XYLITOL; SUCROSE; SUCRALOSE; XANTHAN GUM

HIGHLIGHTS OF PRESCRIBING INFORMATION

These highlights do not include all the information needed to use ZEGERID safely and effectively. See full prescribing information for ZEGERID.
ZEGERID® (omeprazole and sodium bicarbonate) for oral suspension
ZEGERID® (omeprazole and sodium bicarbonate) capsules, for oral use
Initial U.S. Approval: 2004

1 INDICATIONS AND USAGE

ZEGERID is a proton pump inhibitor (PPI).

ZEGERID for oral suspension and ZEGERID capsules are indicated in adults for:

- Treatment of active duodenal ulcer (1)
- Treatment of active benign gastric ulcer (1)
- Treatment of erosive esophagitis (EE) due to acid-mediated gastroesophageal reflux disease (GERD) (1)
- Maintenance of healing of EE (1)

ZEGERID for oral suspension is indicated in adults for:

- Reduction of risk of upper gastrointestinal (GI) bleeding in critically ill patients (1)

2 DOSAGE AND ADMINISTRATION

Indication | Recommended Adult Dosage
ZEGERID for oral suspension or ZEGERID capsules
Active Duodenal Ulcer | 20 mg once daily for 4 weeks; some patients may require an additional 4 weeks
Active Benign Gastric Ulcer | 40 mg once daily for 4 to 8 weeks
Treatment of Symptomatic GERD | 20 mg once daily for up to 4 weeks
Treatment of EE due to Acid-Mediated GERD | 20 mg once daily for 4 to 8 weeks*
Maintenance of Healing of EE due to Acid-Mediated GERD | 20 mg once daily**
40 mg ZEGERID for oral suspension
Reduction of Risk of Upper GI Bleeding in Critically Ill Patients | 40 mg initially followed by 40 mg 6 to 8 hours later and 40 mg once daily thereafter for 14 days

* an additional 4 weeks of treatment may be given if no response; if recurrence, additional 4 to 8-week courses may be considered.

** studied for 12 months.

3 DOSAGE FORMS AND STRENGTHS

For Capsules (3):

- 20 mg omeprazole and 1,100 mg sodium bicarbonate
- 40 mg omeprazole and 1,100 mg sodium bicarbonate

For Oral Suspension (3):

- 20 mg omeprazole and 1,680 mg sodium bicarbonate in unit-dose packets
- 40 mg omeprazole and 1,680 mg sodium bicarbonate in unit-dose packets

4 CONTRAINDICATIONS

- Known hypersensitivity to any components of the formulation (4)
- Patients receiving rilpivirine-containing products (4, 7)

5 WARNINGS AND PRECAUTIONS

- Gastric Malignancy: In adults, symptomatic response does not preclude the presence of gastric malignancy. Consider additional follow-up and diagnostic testing. (5.1)
- Acute Tubulointerstitial Nephritis: Discontinue treatment and evaluate patients. (5.2)
- Sodium Bicarbonate Buffer Content: Take sodium content into consideration in patients on a sodium-restricted diet. Avoid in patients with Bartter’s syndrome, hypokalemia, hypocalcemia, and problems with acid-base balance. (5.3)
- Clostridium difficile-Associated Diarrhea: PPI therapy may be associated with increased risk. (5.4)
- Bone Fracture: Long-term and multiple daily dose PPI therapy may be associated with an increased risk for osteoporosis-related fractures of the hip, wrist, or spine. (5.5)
- Severe Cutaneous Adverse Reactions: Discontinue at the first signs or symptoms of severe cutaneous adverse reactions or other signs of hypersensitivity and consider further evaluation. (5.6)
- Cutaneous and Systemic Lupus Erythematosus: Mostly cutaneous; new onset or exacerbation of existing disease; discontinue ZEGERID and refer to specialist for evaluation. (5.7)
- Interaction with Clopidogrel: Avoid concomitant use of ZEGERID. (5.8)
- Cyanocobalamin (Vitamin B-12) Deficiency: Daily long-term use (e.g., longer than 3 years) may lead to malabsorption or a deficiency of cyanocobalamin. (5.9)
- Hypomagnesemia and Mineral Metabolism: Reported rarely with prolonged treatment with PPIs. (5.10)
- Interaction with St. John’s wort or Rifampin: Avoid concomitant use of ZEGERID. (5.11, 7)
- Interactions with Diagnostic Investigations for Neuroendocrine Tumors: Increased Chromogranin A (CgA) levels may interfere with diagnostic investigations for neuroendocrine tumors; temporarily stop ZEGERID at least 14 days before assessing CgA levels. (5.12)
- Interaction with Methotrexate: Concomitant use with PPIs may elevate and/or prolong serum concentrations of methotrexate and/or its metabolite, possibly leading to toxicity. With high dose methotrexate administration, consider a temporary withdrawal of ZEGERID. (5.13, 7)
- Fundic Gland Polyps: Risk increases with long-term use, especially beyond one year. Use the shortest duration of therapy. (5.14)

6 ADVERSE REACTIONS

Most common adverse reactions (≥2%) are: headache, abdominal pain, nausea, diarrhea, vomiting, and flatulence. (6.1)

To report SUSPECTED ADVERSE REACTIONS, contact Salix Pharmaceuticals at 1-800-321-4576 or FDA at 1-800-FDA-1088 or www.fda.gov/medwatch.

7 DRUG INTERACTIONS

See full prescribing information for a list of clinically important drug interactions. (7)

8 USE IN SPECIFIC POPULATIONS

Hepatic Impairment and Asian Patients: Avoid use for maintenance of healing of erosive esophagitis. (8.6, 8.7)

FULL PRESCRIBING INFORMATION

1 INDICATIONS AND USAGE

ZEGERID for oral suspension and ZEGERID capsules are indicated in adults for the:

- short-term treatment of active duodenal ulcer. Most patients heal within four weeks. Some patients may require an additional four weeks of therapy.
- short-term treatment (4 to 8 weeks) of active benign gastric ulcer.
- treatment of heartburn and other symptoms associated with GERD for up to 4 weeks.
- short-term treatment (4 to 8 weeks) of EE due to acid-mediated GERD which has been diagnosed by endoscopy in adults.
  - The efficacy of ZEGERID used for longer than 8 weeks in patients with EE has not been established. If a patient does not respond to 8 weeks of treatment, an additional 4 weeks of treatment may be given. If there is recurrence of EE or GERD symptoms (e.g., heartburn), additional 4 to 8-week courses of ZEGERID may be considered.
- maintenance of healing of EE due to acid-mediated GERD. Controlled studies do not extend beyond 12 months.

ZEGERID for oral suspension is indicated in adults for the:

- reduction of risk of upper GI bleeding in critically ill adult patients.

2 DOSAGE AND ADMINISTRATION

2.1 Important Administration Instructions

- ZEGERID (omeprazole and sodium bicarbonate) is available as a capsule and as a powder for oral suspension in 20 mg and 40 mg strengths of omeprazole for adult use. All recommended doses throughout the labeling are based upon omeprazole.
- The sodium content of ZEGERID capsules and ZEGERID for oral suspension should be taken into consideration when prescribing this product [see Warnings and Precautions (5.3)]:
  - ZEGERID capsule: each 20 mg and 40 mg capsule contains 1,100 mg (13 mEq) of sodium bicarbonate. The total content of sodium in each capsule is 304 mg.
  - ZEGERID for oral suspension: each 20 mg and 40 mg packet of contains 1,680 mg (20 mEq) of sodium bicarbonate. The total content of sodium in each packet is 460 mg.
- Due to the sodium bicarbonate content of ZEGERID:
- Do not substitute two packets of 20 mg ZEGERID for oral suspension with one packet of 40 mg ZEGERID for oral suspension.
- Do not substitute two 20 mg ZEGERID capsules with one 40 mg ZEGERID capsule.

2.2 Dosage Regimen

The recommended dosage regimen by indication in adults of ZEGERID for oral suspension and ZEGERID capsules is summarized in Table 1. Only 40 mg ZEGERID for oral suspension is indicated for the reduction of risk of upper GI bleeding in critically ill adult patients and the dosage regimen is summarized in Table 2. All recommended dosages are based upon omeprazole content.

Table 1: Recommended Dosage Regimen of ZEGERID for Oral Suspension and ZEGERID Capsules in Adults by Indication
Indication | Dosage of; ZEGERID for oral suspension or ZEGERID capsules | Treatment Duration
Treatment of Active Duodenal Ulcer | 20 mg once daily | 4 weeks [Most patients heal within 4 weeks. Some patients may require an additional 4 weeks of therapy [see Clinical Studies (14.1)].] [The efficacy of ZEGERID used for longer than 8 weeks in patients with EE has not been established. If a patient does not respond to 8 weeks of treatment, an additional 4 weeks of treatment may be given. If there is recurrence of EE or GERD symptoms (e.g., heartburn), additional 4 to 8-week courses of ZEGERID may be considered.]
Treatment of Active Benign Gastric Ulcer | 40 mg once daily | 4 to 8 weeks
Treatment of Symptomatic GERD | 20 mg once daily | Up to 4 weeks
Treatment of EE due to Acid-Mediated GERD | 20 mg once daily | 4 to 8 weeks
Maintenance of Healing of EE due to Acid-Mediated GERD | 20 mg once daily | Controlled studies do not extend beyond 12 months.

Table 2: Recommended Dosage Regimen of 40 mg ZEGERID for Oral Suspension in Adults by Indication
Indication | Dosage of; 40 mg ZEGERID for oral suspension | Treatment Duration
Reduction of Risk of Upper GI Bleeding in Critically Ill Patients | 40 mg initially; followed by 40 mg 6 to 8 hours later; and 40 mg once daily thereafter | 14 days

2.3 Preparation and Administration

ZEGERID Capsules

- Swallow capsules intact with water. Do not open the capsule and do not administer with liquids other than water.
- Take on an empty stomach at least one hour before a meal [see Clinical Pharmacology (12.3)].

ZEGERID for Oral Suspension

- ZEGERID for oral suspension is intended to be mixed with water and administered orally or via a nasogastric (NG) or orogastric (OG) tube.
- If administered orally, take on an empty stomach at least one hour before a meal.
- If administered via NG or OG tube, suspend enteral feeding approximately 3 hours before and 1 hour after administration of ZEGERID for oral suspension.

Oral Administration

- Empty the contents of a packet into a small cup containing 5 to 10 mL of water. Do not mix with liquids or foods other than water.
- Stir well and drink immediately.
- Refill cup with water and drink immediately.

Nasogastric (NG) or Orogastric (OG) Tube Administration

- Add 20 mL of water to a catheter tipped syringe and then add the contents of a packet. Use an appropriately-sized catheter tipped syringe. Do not mix with liquids or foods other than water.
- Shake the syringe to dissolve the powder.
- Administer through the NG or orogastric tube into the stomach right away.
- Refill the syringe with an equal amount of water.
- Shake and flush any remaining contents from the NG tube or orogastric tube into the stomach.

3 DOSAGE FORMS AND STRENGTHS

ZEGERID is available as:

Capsules

- 20 mg: Each opaque, hard gelatin, white capsule, imprinted with the Santarus logo and “20”, contains 20 mg omeprazole and 1,100 mg sodium bicarbonate.
- 40 mg: Each opaque, hard gelatin, colored dark blue and white capsule, imprinted with the Santarus logo and “40”, contains 40 mg omeprazole and 1,100 mg sodium bicarbonate.

For Oral Suspension

- 20 mg: white, flavored powder packaged in unit-dose packets. Each packet contains 20 mg omeprazole and 1,680 mg sodium bicarbonate.
- 40 mg: white, flavored powder packaged in unit-dose packets. Each packet contains 40 mg omeprazole and 1,680 mg sodium bicarbonate.

4 CONTRAINDICATIONS

ZEGERID is contraindicated in patients with known hypersensitivity to substituted benzimidazoles or to any component of the formulation. Hypersensitivity reactions may include anaphylaxis, anaphylactic shock, angioedema, bronchospasm, acute tubulointerstitial nephritis, and urticaria [see Warnings and Precautions (5.2), Adverse Reactions (6.2)].

Proton pump inhibitors (PPIs), including ZEGERID, are contraindicated in patients receiving rilpivirine containing products [see Drug Interactions (7)].

5 WARNINGS AND PRECAUTIONS

5.1 Presence of Gastric Malignancy

In adults, symptomatic response to therapy with ZEGERID does not preclude the presence of gastric malignancy. Consider additional follow-up and diagnostic testing in adult patients who have a suboptimal response or an early symptomatic relapse after completing treatment with a proton pump inhibitor (PPI). In older patients, also consider an endoscopy.

5.2 Acute Tubulointerstitial Nephritis

Acute tubulointerstitial nephritis (TIN) has been observed in patients taking PPIs and may occur at any point during PPI therapy. Patients may present with varying signs and symptoms from symptomatic hypersensitivity reactions to non-specific symptoms of decreased renal function (e.g., malaise, nausea and anorexia). In reported case series, some patients were diagnosed on biopsy and in the absence of extra-renal manifestations (e.g., fever, rash or arthralgia).

Discontinue ZEGERID and evaluate patients with suspected acute TIN [see Contraindications (4)].

5.3 Sodium Bicarbonate Buffer Content

Each 20 mg and 40 mg ZEGERID capsule contains 1,100 mg (13 mEq) of sodium bicarbonate. The total content of sodium in each capsule is 304 mg.

Each 20 mg and 40 mg packet of ZEGERID for oral suspension contains 1,680 mg (20 mEq) of sodium bicarbonate. The total content of sodium in each packet is 460 mg.

Chronic administration of bicarbonate with calcium or milk can cause milk-alkali syndrome. Chronic use of sodium bicarbonate may lead to systemic alkalosis, and increased sodium intake can produce edema and weight gain.

The sodium content of ZEGERID products should be taken into consideration when administering to patients on a sodium-restricted diet or those at risk for developing congestive heart failure.

Avoid ZEGERID in patients with Bartter’s syndrome, hypokalemia, hypocalcemia, and problems with acid-base balance.

5.4 Clostridium difficile-Associated Diarrhea

Published observational studies suggest that PPI therapy like ZEGERID may be associated with an increased risk of Clostridium difficile-associated diarrhea, especially in hospitalized patients. This diagnosis should be considered for diarrhea that does not improve [see Adverse Reactions (6.2)].

Patients should use the lowest dose and shortest duration of PPI therapy appropriate to the condition being treated.

5.5 Bone Fracture

Several published observational studies suggest that proton pump inhibitor (PPI) therapy may be associated with an increased risk for osteoporosis-related fractures of the hip, wrist, or spine. The risk of fracture was increased in patients who received high-dose, defined as multiple daily doses, and long-term PPI therapy (a year or longer). Patients should use the lowest dose and shortest duration of PPI therapy appropriate to the condition being treated. Patients at risk for osteoporosis-related fractures should be managed according to the established treatment guidelines [see Dosage and Administration (2.2) and Adverse Reactions (6.2)].

5.6 Severe Cutaneous Adverse Reactions

Severe cutaneous adverse reactions, including Stevens-Johnson syndrome (SJS) and toxic epidermal necrolysis (TEN), drug reaction with eosinophilia and systemic symptoms (DRESS), and acute generalized exanthematous pustulosis (AGEP) have been reported in association with the use of PPIs [see Adverse Reactions (6.2)]. Discontinue ZEGERID at the first signs or symptoms of severe cutaneous adverse reactions or other signs of hypersensitivity and consider further evaluation.

5.7 Cutaneous and Systemic Lupus Erythematosus

Cutaneous lupus erythematosus (CLE) and systemic lupus erythematosus (SLE) have been reported in patients taking PPIs, including omeprazole. These events have occurred as both new onset and an exacerbation of existing autoimmune disease. The majority of PPI-induced lupus erythematosus cases were CLE.

The most common form of CLE reported in patients treated with PPIs was subacute CLE (SCLE) and occurred within weeks to years after continuous drug therapy in patients ranging from infants to the elderly. Generally, histological findings were observed without organ involvement.

Systemic lupus erythematosus (SLE) is less commonly reported than CLE in patients receiving PPIs. PPI associated SLE is usually milder than non-drug induced SLE. Onset of SLE typically occurred within days to years after initiating treatment in patients ranging from young adults to the elderly. The majority of patients presented with rash; however, arthralgia and cytopenia were also reported.

Avoid administration of PPIs for longer than medically indicated. If signs or symptoms consistent with CLE or SLE are noted in patients receiving ZEGERID, discontinue the drug and refer the patient to the appropriate specialist for evaluation. Most patients improve with discontinuation of the PPI alone in 4 to 12 weeks. Serological testing (e.g., ANA) may be positive and elevated serological test results may take longer to resolve than clinical manifestations.

5.8 Interaction with Clopidogrel

Avoid concomitant use of ZEGERID with clopidogrel. Clopidogrel is a prodrug. Inhibition of platelet aggregation by clopidogrel is entirely due to an active metabolite. The metabolism of clopidogrel to its active metabolite can be impaired by use with concomitant medications, such as omeprazole, that interfere with CYP2C19 activity. Concomitant use of clopidogrel with 80 mg omeprazole reduces the pharmacological activity of clopidogrel, even when administered 12 hours apart. When using ZEGERID, consider alternative antiplatelet therapy [see Drug Interactions (7) and Clinical Pharmacology (12.3)].

5.9 Cyanocobalamin (Vitamin B-12) Deficiency

Daily treatment with any acid-suppressing medications over a long period of time (e.g., longer than 3 years) may lead to malabsorption of cyanocobalamin (vitamin B-12) caused by hypo- or achlorhydria. Rare reports of cyanocobalamin deficiency occurring with acid-suppressing therapy have been reported in the literature. This diagnosis should be considered if clinical symptoms consistent with cyanocobalamin deficiency are observed in patients treated with ZEGERID.

5.10 Hypomagnesemia and Mineral Metabolism

Hypomagnesemia, symptomatic and asymptomatic, has been reported rarely in patients treated with PPIs for at least three months, in most cases after a year of therapy. Serious adverse events include tetany, arrhythmias, and seizures. Hypomagnesemia may lead to hypocalcemia and/or hypokalemia and may exacerbate underlying hypocalcemia in at-risk patients. In most patients, treatment of hypomagnesemia required magnesium replacement and discontinuation of the PPI.

For patients expected to be on prolonged treatment or who take PPIs with medications such as digoxin or drugs that may cause hypomagnesemia (e.g., diuretics), health care professionals may consider monitoring magnesium levels prior to initiation of PPI treatment and periodically [see Adverse Reactions (6.2)].

Consider monitoring magnesium and calcium levels prior to initiation of ZEGERID and periodically while on treatment in patients with a preexisting risk of hypocalcemia (e.g., hypoparathyroidism). Supplement with magnesium and/or calcium as necessary. If hypocalcemia is refractory to treatment, consider discontinuing the PPI.

5.11 Interaction with St. John’s wort or Rifampin

Drugs which induce CYP2C19 or CYP3A4 (such as St. John’s wort or rifampin) can substantially decrease omeprazole concentrations [see Drug Interactions (7)]. Avoid concomitant use of ZEGERID with St. John’s wort or rifampin.

5.12 Interactions with Investigations for Neuroendocrine Tumors

Serum chromogranin A (CgA) levels increase secondary to drug-induced decreases in gastric acidity. The increased CgA level may cause false positive results in diagnostic investigations for neuroendocrine tumors. Providers should temporarily stop ZEGERID treatment for at least 14 days before assessing CgA levels and consider repeating the test if initial CgA levels are high. If serial tests are performed (e.g., for monitoring), the same commercial laboratory should be used for testing, as reference ranges between tests may vary [see Drug Interactions (7)].

5.13 Interaction with Methotrexate

Literature suggests that concomitant use of PPIs with methotrexate (primarily at high dose) may elevate and prolong serum levels of methotrexate and/or its metabolite, possibly leading to methotrexate toxicities. In high-dose methotrexate administration, a temporary withdrawal of the PPI may be considered in some patients [see Drug Interactions (7)].

5.14 Fundic Gland Polyps

PPI use is associated with an increased risk of fundic gland polyps that increases with long-term use, especially beyond one year. Most PPIs users who developed fundic gland polyps were asymptomatic and fundic gland polyps were identified incidentally on endoscopy. Use the shortest duration of PPI therapy appropriate to the condition being treated.

6 ADVERSE REACTIONS

The following serious adverse reactions are described below and elsewhere in labeling:

- Acute Tubulointerstitial Nephritis [see Warnings and Precautions (5.2)]
- Clostridium difficile-Associated Diarrhea [see Warnings and Precautions (5.4)]
- Bone Fracture [see Warnings and Precautions (5.5)]
- Severe Cutaneous Adverse Reactions [see Warnings and Precautions (5.6)]
- Cutaneous and Systemic Lupus Erythematosus [see Warnings and Precautions (5.7)]
- Cyanocobalamin (Vitamin B-12) Deficiency [see Warnings and Precautions (5.9)]
- Hypomagnesemia and Mineral Metabolism [see Warnings and Precautions (5.10)]
- Fundic Gland Polyps [see Warnings and Precautions (5.14)]

6.1 Clinical Trials Experience

Because clinical trials are conducted under widely varying conditions, adverse reaction rates observed in the clinical trials of a drug cannot be directly compared to rates in the clinical trials of another drug and may not reflect the rates observed in practice.

The safety of ZEGERID has been established, in part, based on oral studies of an oral delayed-release omeprazole product.

Clinical Trials with Omeprazole

In the U.S. clinical trial population of 465 adult patients, the adverse reactions summarized in Table 3 were reported to occur in 1% or more of patients on therapy with omeprazole.

Table 3: Adverse Reactions Occurring in 1% or More of Adult Patients in US Clinical Trials of Omeprazole Therapy
 | Omeprazole; % (n = 465) | Placebo; % (n = 64) | Ranitidine; % (n = 195)
Headache | 7 | 6 | 8
Diarrhea | 3 | 3 | 2
Abdominal Pain | 2 | 3 | 3
Nausea | 2 | 3 | 4
Upper Respiratory Infection (URI) | 2 | 2 | 3
Dizziness | 2 | 0 | 3
Vomiting | 2 | 5 | 2
Rash | 2 | 0 | 0
Constipation | 1 | 0 | 0
Cough | 1 | 0 | 2
Asthenia | 1 | 2 | 2
Back Pain | 1 | 0 | 1

Table 4 summarizes the adverse reactions that occurred in 1% or more of omeprazole-treated patients from international double-blind and open-label clinical trials in which 2,631 patients and subjects received omeprazole.

Table 4: Adverse Reactions Occurring in 1% or More of Adult Patients in International Clinical Trials of Omeprazole Therapy
 | Omeprazole; % (N = 2631) | Placebo; % (N = 120)
Abdominal Pain | 5.2 | 3.3
Nausea | 4.0 | 6.7
Diarrhea | 3.7 | 2.5
Vomiting | 3.2 | 10.0
Headache | 2.9 | 2.5
Flatulence | 2.7 | 5.8
Acid Regurgitation | 1.9 | 3.3
Constipation | 1.5 | 0.8
Asthenia | 1.3 | 0.8

Clinical Trial of 40 mg ZEGERID for Oral Suspension

Adverse reactions reported in at least 3% of critically ill adult patients in a clinical trial of 40 mg ZEGERID for oral suspension compared to intravenous cimetidine for up to 14 days are presented in Table 5.

Table 5: Common Adverse Reactions [reported in at least 3% of patients in either treatment group.] by Body System and Preferred Term in a Randomized Controlled Trial of Critically Ill Adult Patients Treated up to 14 Days
Body System; Preferred Term | ZEGERID; 40 mg for oral suspension once daily; % (N=178) | Intravenous Cimetidine; 1,200 mg per day; % (N=181)
Blood and Lymphatic System Disorders
Anemia NOS | 7.9 | 7.7
Anemia NOS Aggravated | 2.2 | 3.9
Thrombocytopenia | 10.1 | 6.1
Cardiac Disorders
Atrial Fibrillation | 6.2 | 3.9
Bradycardia NOS | 3.9 | 2.8
Supraventricular Tachycardia | 3.4 | 1.1
Tachycardia NOS | 3.4 | 3.3
Ventricular Tachycardia | 4.5 | 3.3
Gastrointestinal Disorders [In this trial, clinically significant upper gastrointestinal bleeding was considered a serious adverse reaction, but it is not included in this table.]
Constipation | 4.5 | 4.4
Diarrhea NOS | 3.9 | 8.3
Gastric Hypomotility | 1.7 | 3.3
General Disorders and Administration Site Conditions
Hyperpyrexia | 4.5 | 1.7
Edema NOS | 2.8 | 6.1
Pyrexia | 20.2 | 16.0
Infections and Infestations
Candidal Infection NOS | 1.7 | 3.9
Oral Candidiasis | 3.9 | 0.6
Sepsis NOS | 5.1 | 5.0
Urinary Tract Infection | 2.2 | 3.3
Investigations
Liver Function Tests NOS Abnormal | 1.7 | 3.3
Metabolism and Nutrition Disorders
Fluid Overload | 5.1 | 7.7
Hyperglycemia NOS | 10.7 | 11.6
Hyperkalemia | 2.2 | 3.3
Hypernatremia | 1.7 | 5.0
Hypocalcemia | 6.2 | 5.5
Hypoglycemia NOS | 3.4 | 4.4
Hypokalemia | 12.4 | 13.3
Hypomagnesemia | 10.1 | 9.9
Hyponatremia | 3.9 | 2.8
Hypophosphatemia | 6.2 | 3.9
Psychiatric Disorders
Agitation | 3.4 | 8.8
Respiratory, Thoracic and Mediastinal Disorders
Acute Respiratory Distress Syndrome | 3.4 | 3.9
Nosocomial Pneumonia | 11.2 | 9.4
Pneumothorax NOS | 0.6 | 4.4
Respiratory Failure | 1.7 | 3.3
Skin and Subcutaneous Tissue Disorders
Decubitus Ulcer | 3.4 | 2.8
Rash NOS | 5.6 | 6.1
Vascular Disorders
Hypertension NOS | 7.9 | 3.3
Hypotension NOS | 9.6 | 6.6
NOS = not otherwise specified

6.2 Postmarketing Experience

The following adverse reactions have been identified during post-approval use of omeprazole and sodium bicarbonate. Because these reactions are reported voluntarily from a population of uncertain size, it is not always possible to reliably estimate their frequency or establish a causal relationship to drug exposure.

Omeprazole

Body as a Whole: Hypersensitivity reactions, including anaphylaxis, anaphylactic shock, angioedema, bronchospasm, urticaria (see also Skin below), fever, pain, fatigue, malaise, and systemic lupus erythematosus.

Cardiovascular: Chest pain or angina, tachycardia, bradycardia, palpitation, elevated blood pressure, and peripheral edema.

Gastrointestinal: Pancreatitis (some fatal), anorexia, irritable colon, flatulence, fecal discoloration, esophageal candidiasis, mucosal atrophy of the tongue, dry mouth, stomatitis, abdominal swelling and fundic gland polyps. Gastroduodenal carcinoids have been reported in patients with Zollinger-Ellison syndrome on long-term treatment with omeprazole. This finding is believed to be a manifestation of the underlying condition, which is known to be associated with such tumors.

Hepatic: Mild and, rarely, marked elevations of liver function tests [ALT (SGPT), AST (SGOT), ᵞ-glutamyl transpeptidase, alkaline phosphatase, and bilirubin (jaundice)]. In rare instances, overt liver disease has occurred, including hepatocellular, cholestatic, or mixed hepatitis, liver necrosis (some fatal), hepatic failure (some fatal), and hepatic encephalopathy.

Infections and Infestations: Clostridium difficile-associated diarrhea.

Metabolism and Nutritional Disorders: Hypomagnesemia, hypocalcemia, hypokalemia [see Warnings and Precautions (5.10)], hyponatremia, hypoglycemia, and weight gain.

Musculoskeletal: Muscle cramps, myalgia, muscle weakness, joint pain, bone fracture, and leg pain.

Nervous System/Psychiatric: Psychic disturbances including depression, agitation, aggression, hallucinations, confusion, insomnia, nervousness, tremors, apathy, somnolence, anxiety, dream abnormalities; vertigo; paresthesia; and hemifacial dysesthesia.

Respiratory: Epistaxis, pharyngeal pain.

Skin: Severe generalized skin reactions including TEN (some fatal), SJS, DRESS, AGEP, cutaneous lupus erythematosus and erythema multiforme (some severe); purpura and/or petechiae (some with rechallenge); skin inflammation, urticaria, angioedema, pruritus, photosensitivity, alopecia, dry skin, and hyperhidrosis.

Special Senses: Tinnitus, taste perversion.

Ocular: Blurred vision, ocular irritation, dry eye syndrome, optic atrophy, anterior ischemic optic neuropathy, optic neuritis, and double vision.

Urogenital: Tubulointerstitial nephritis, urinary tract infection, microscopic pyuria, urinary frequency, elevated serum creatinine, proteinuria, hematuria, glycosuria, testicular pain, gynecomastia, and erectile dysfunction.

Hematologic: Rare instances of pancytopenia, agranulocytosis (some fatal), thrombocytopenia, neutropenia, leukopenia, anemia, leukocytosis, and hemolytic anemia have been reported.

Sodium Bicarbonate

Metabolic alkalosis, seizures, and tetany.

7 DRUG INTERACTIONS

Tables 6 and 7 include drugs with clinically important drug interactions and interaction with diagnostics when administered concomitantly with omeprazole and instructions for preventing or managing them.

Consult the labeling of concomitantly used drugs to obtain further information about interactions with PPIs.

Table 6: Clinically Relevant Interactions Affecting Drugs Co-Administered with Omeprazole and Interaction with Diagnostics
Antiretrovirals
Clinical Impact: | The effect of PPIs on antiretroviral drugs is variable. The clinical importance and the mechanisms behind these interactions are not always known.; - Decreased exposure of some antiretroviral drugs (e.g., rilpivirine, atazanavir and nelfinavir) when used concomitantly with omeprazole may reduce antiviral effect and promote the development of drug resistance [see Clinical Pharmacology (12.3)]. - Increased exposure of other antiretroviral drugs (e.g., saquinavir) when used concomitantly with omeprazole may increase toxicity [see Clinical Pharmacology (12.3)]. - There are other antiretroviral drugs which do not result in clinically relevant interactions with omeprazole.
Intervention: | Rilpivirine-containing products: Concomitant use with ZEGERID is contraindicated [see Contraindications (4)].; Atazanavir: Avoid concomitant use with ZEGERID. See prescribing information for atazanavir for dosing information.; Nelfinavir: Avoid concomitant use with ZEGERID. See prescribing information for nelfinavir.; Saquinavir: See the prescribing information for saquinavir for monitoring of potential saquinavir-related toxicities.; Other antiretrovirals: See prescribing information for specific antiretroviral drugs.
Warfarin
Clinical Impact: | Increased INR and prothrombin time in patients receiving PPIs, including omeprazole, and warfarin concomitantly. Increases in INR and prothrombin time may lead to abnormal bleeding and even death.
Intervention: | Monitor INR and prothrombin time and adjust the dose of warfarin, if needed, to maintain target INR range.
Methotrexate
Clinical Impact: | Concomitant use of omeprazole with methotrexate (primarily at high dose) may elevate and prolong serum concentrations of methotrexate and/or its metabolite hydroxymethotrexate, possibly leading to methotrexate toxicities. No formal drug interaction studies of high-dose methotrexate with PPIs have been conducted [see Warnings and Precautions (5.13)].
Intervention: | A temporary withdrawal of ZEGERID may be considered in some patients receiving high-dose methotrexate.
CYP2C19 Substrates (e.g., clopidogrel, citalopram, cilostazol, phenytoin, diazepam)
Clopidogrel
Clinical Impact: | Concomitant use of omeprazole 80 mg results in reduced plasma concentrations of the active metabolite of clopidogrel and a reduction in platelet inhibition [see Clinical Pharmacology (12.3)].; There are no adequate combination studies of a lower dose of omeprazole or a higher dose of clopidogrel in comparison with the approved dose of clopidogrel.
Intervention: | Avoid concomitant use with ZEGERID. Consider use of alternative anti-platelet therapy [see Warnings and Precautions (5.8)].
Citalopram
Clinical Impact: | Increased exposure of citalopram leading to an increased risk of QT prolongation [see Clinical Pharmacology (12.3)].
Intervention: | Limit the dose of citalopram to a maximum of 20 mg per day. See prescribing information for citalopram.
Cilostazol
Clinical Impact: | Increased exposure of one of the active metabolites of cilostazol (3,4-dihydro-cilostazol) [see Clinical Pharmacology (12.3)].
Intervention: | Reduce the dose of cilostazol to 50 mg twice daily. See prescribing information for cilostazol.
Phenytoin
Clinical Impact: | Potential for increased exposure of phenytoin.
Intervention: | Monitor phenytoin serum concentrations. Dose adjustment may be needed to maintain therapeutic drug concentrations. See prescribing information for phenytoin.
Diazepam
Clinical Impact: | Increased exposure of diazepam [see Clinical Pharmacology (12.3)].
Intervention: | Monitor patients for increased sedation and reduce the dose of diazepam as needed.
Digoxin
Clinical Impact: | Potential for increased exposure of digoxin [see Clinical Pharmacology (12.3)].
Intervention: | Monitor digoxin concentrations. Dose adjustment may be needed to maintain therapeutic drug concentrations. See digoxin prescribing information.
Drugs Dependent on Gastric pH for Absorption (e.g., iron salts, erlotinib, dasatinib, nilotinib, mycophenolate mofetil, ketoconazole/itraconazole)
Clinical Impact: | Omeprazole can reduce the absorption of other drugs due to its effect on reducing intragastric acidity.
Intervention: | Mycophenolate mofetil (MMF): Co-administration of omeprazole in healthy subjects and in transplant patients receiving MMF has been reported to reduce the exposure to the active metabolite, mycophenolic acid (MPA), possibly due to a decrease in MMF solubility at an increased gastric pH. The clinical relevance of reduced MPA exposure on organ rejection has not been established in transplant patients receiving ZEGERID and MMF. Use ZEGERID with caution in transplant patients receiving MMF [see Clinical Pharmacology (12.3)].; See the prescribing information for other drugs dependent on gastric pH for absorption.
Tacrolimus
Clinical Impact: | Potential for increased exposure of tacrolimus, especially in transplant patients who are intermediate or poor metabolizers of CYP2C19.
Intervention: | Monitor tacrolimus whole blood concentrations. Dose adjustment may be needed to maintain therapeutic drug concentrations. See prescribing information for tacrolimus.
Interactions with Investigations of Neuroendocrine Tumors
Clinical Impact: | Serum chromogranin A (CgA) levels increase secondary to PPI-induced decreases in gastric acidity. The increased CgA level may cause false positive results in diagnostic investigations for neuroendocrine tumors [see Warnings and Precautions (5.12) and Clinical Pharmacology (12.2)].
Intervention: | Temporarily stop PRILOSEC treatment at least 14 days before assessing CgA levels and consider repeating the test if initial CgA levels are high. If serial tests are performed (e.g., for monitoring), the same commercial laboratory should be used for testing, as reference ranges between tests may vary.
Interaction with Secretin Stimulation Test
Clinical Impact: | Hyper-response in gastrin secretion in response to secretin stimulation test, falsely suggesting gastrinoma.
Intervention: | Temporarily stop ZEGERID treatment at least 14 days before assessing to allow gastrin levels to return to baseline [see Clinical Pharmacology (12.2)].
False Positive Urine Tests for THC
Clinical Impact: | There have been reports of false positive urine screening tests for tetrahydrocannabinol (THC) in patients receiving PPIs.
Intervention: | An alternative confirmatory method should be considered to verify positive results.
Other
Clinical Impact: | There have been clinical reports of interactions with other drugs metabolized via the cytochrome P450 system (e.g., cyclosporine, disulfiram).
Intervention: | Monitor patients to determine if it is necessary to adjust the dosage of these other drugs when taken concomitantly with ZEGERID.

Table 7: Clinically Relevant Interactions Affecting Omeprazole When Co-Administered with Other Drugs
CYP2C19 or CYP3A4 Inducers
Clinical Impact: | Decreased exposure of omeprazole when used concomitantly with strong inducers [see Clinical Pharmacology (12.3)].
Intervention: | St. John’s wort, rifampin: Avoid concomitant use with ZEGERID [see Warnings and Precautions (5.11)].; Ritonavir-containing products: See prescribing information for specific drugs.
CYP2C19 or CYP3A4 Inhibitors
Clinical Impact: | Increased exposure of omeprazole [see Clinical Pharmacology (12.3)].
Intervention: | Voriconazole: Dosage adjustment of ZEGERID is not required.

8 USE IN SPECIFIC POPULATIONS

8.1 Pregnancy

Risk Summary

There are no adequate and well-controlled studies with ZEGERID in pregnant women. ZEGERID contains omeprazole and sodium bicarbonate.

Omeprazole

There are no adequate and well-controlled studies with omeprazole in pregnant women. Available epidemiologic data fail to demonstrate an increased risk of major congenital malformations or other adverse pregnancy outcomes with first trimester omeprazole use. Reproduction studies in rats and rabbits resulted in dose-dependent embryo-lethality at omeprazole doses that were approximately 3.4 to 34 times an oral human dose of 40 mg (based on a body surface area for a 60 kg person).

Teratogenicity was not observed in animal reproduction studies with administration of oral esomeprazole (an enantiomer of omeprazole) magnesium in rats and rabbits during organogenesis with doses about 68 times and 42 times, respectively, an oral human dose of 40 mg esomeprazole or 40 mg omeprazole (based on body surface area for a 60 kg person). Changes in bone morphology were observed in offspring of rats dosed through most of pregnancy and lactation at doses equal to or greater than approximately 34 times an oral human dose of 40 mg esomeprazole or 40 mg omeprazole. When maternal administration was confined to gestation only, there were no effects on bone physeal morphology in the offspring at any age (see Data).

Sodium Bicarbonate

Available data with sodium bicarbonate use in pregnant women are insufficient to identify a drug associated risk of major birth defects or miscarriage. Published animal studies report that sodium bicarbonate administered to rats, mice or rabbits during pregnancy did not cause adverse developmental effects in offspring.

The estimated background risks of major birth defects and miscarriage for the indicated population are unknown. All pregnancies have a background risk of birth defect, loss or other adverse outcomes. In the U.S. general population, the estimated background risk of major birth defects and miscarriage in clinically recognized pregnancies is 2% to 4% and 15% to 20%, respectively.

Data

Human Data

There are no adequate and well-controlled studies with ZEGERID in pregnant women. Four published epidemiological studies compared the frequency of congenital abnormalities among infants born to women who used omeprazole during pregnancy with the frequency of abnormalities among infants of women exposed to H2-receptor antagonists or other controls.

A population-based retrospective cohort epidemiological study from the Swedish Medical Birth Register, covering approximately 99% of pregnancies, from 1995-99, reported on 955 infants (824 exposed during the first trimester with 39 of these exposed beyond first trimester, and 131 exposed after the first trimester) whose mothers used omeprazole during pregnancy. The number of infants exposed in utero to omeprazole that had any malformation, low birth weight, low Apgar score, or hospitalization was similar to the number observed in this population. The number of infants born with ventricular septal defects and the number of stillborn infants was slightly higher in the omeprazole-exposed infants than the expected number in this population.

A population-based retrospective cohort study covering all live births in Denmark from 1996-2009 reported on 1,800 live births whose mothers used omeprazole during the first trimester of pregnancy and 837,317 live births whose mothers did not use any PPI. The overall rate of birth defects in infants born to mothers with first trimester exposure to omeprazole was 2.9% and 2.6% in infants born to mothers not exposed to any PPI during the first trimester.

A retrospective cohort study reported on 689 pregnant women exposed to either H2-blockers or omeprazole in the first trimester (134 exposed to omeprazole) and 1,572 pregnant women unexposed to either during the first trimester. The overall malformation rate in offspring born to mothers with first trimester exposure to omeprazole, an H2-blocker, or were unexposed was 3.6%, 5.5%, and 4.1%, respectively.

A small prospective observational cohort study followed 113 women exposed to omeprazole during pregnancy (89% first trimester exposures). The reported rate of major congenital malformations was 4% in the omeprazole group, 2% in controls exposed to non-teratogens, and 2.8% in disease-paired controls. Rates of spontaneous and elective abortions, preterm deliveries, gestational age at delivery, and mean birth weight were similar among the groups.

Several studies have reported no apparent adverse short-term effects on the infant when single-dose oral or intravenous omeprazole was administered to over 200 pregnant women as premedication for cesarean section under general anesthesia.

Animal Data

Omeprazole

Reproductive studies conducted with omeprazole in rats at oral doses up to 138 mg/kg/day (about 34 times an oral human dose of 40 mg on a body surface area basis) and in rabbits at doses up to 69.1 mg/kg/day (about 34 times an oral human dose of 40 mg on a body surface area basis) during organogenesis did not disclose any evidence for a teratogenic potential of omeprazole. In rabbits, omeprazole in a dose range of 6.9 to 69.1 mg/kg/day (about 3.4 to 34 times an oral human dose of 40 mg on a body surface area basis) administered during organogenesis produced dose-related increases in embryo-lethality, fetal resorptions, and pregnancy disruptions. In rats, dose-related embryo/fetal toxicity and postnatal developmental toxicity were observed in offspring resulting from parents treated with omeprazole at 13.8 to 138 mg/kg/day (about 3.4 to 34 times an oral human dose of 40 mg on a body surface area basis), administered prior to mating through the lactation period.

Esomeprazole

The data described below was generated from studies using esomeprazole, an enantiomer of omeprazole. The animal to human dose multiples are based on the assumption of equal systemic exposure to esomeprazole in humans following oral administration of either 40 mg esomeprazole or 40 mg omeprazole.

No effects on embryo-fetal development were observed in reproduction studies with esomeprazole magnesium in rats at oral doses up to 280 mg/kg/day (about 68 times an oral human dose of 40 mg on a body surface area basis) and in rabbits at oral doses up to 86 mg/kg/day (about 42 times an oral human dose of 40 mg of esomeprazole or 40 mg omeprazole on a body surface area basis) administered during organogenesis.

A pre- and postnatal developmental toxicity study in rats with additional endpoints to evaluate bone development were performed with esomeprazole magnesium at oral doses of 14 to 280 mg/kg/day (about 3.4 to 68 times an oral human dose of 40 mg of esomeprazole or 40 mg omeprazole on a body surface area basis). Neonatal/early postnatal (birth to weaning) survival was decreased at doses equal to or greater than 138 mg/kg/day (about 34 times an oral human dose of 40 mg esomeprazole or 40 mg omeprazole on a body surface area basis). Body weight and body weight gain were reduced and neurobehavioral or general developmental delays in the immediate post-weaning timeframe were evident at doses equal to or greater than 69 mg/kg/day (about 17 times an oral human dose of 40 mg esomeprazole or 40 mg omeprazole on a body surface area basis). In addition, decreased femur length, width and thickness of cortical bone, decreased thickness of the tibial growth plate and minimal to mild bone marrow hypocellularity were noted at doses of esomeprazole magnesium equal to or greater than 14 mg/kg/day (about 3.4 times an oral human dose of 40 mg esomeprazole or 40 mg omeprazole on a body surface area basis). Physeal dysplasia in the femur was observed in offspring of rats treated with oral doses of esomeprazole magnesium at doses equal to or greater than 138 mg/kg/day (about 34 times an oral human dose of 40 mg esomeprazole or 40 mg omeprazole on a body surface area basis).

Effects on maternal bone were observed in pregnant and lactating rats in a pre- and postnatal toxicity study when esomeprazole magnesium was administered at oral doses of 14 to 280 mg/kg/day (about 3.4 to 68 times an oral human dose of 40 mg esomeprazole or 40 mg omeprazole on a body surface area basis). When rats were dosed from gestational Day 7 through weaning on postnatal Day 21, a statistically significant decrease in maternal femur weight of up to 14% (as compared to placebo treatment) was observed at doses of esomeprazole magnesium equal to or greater than 138 mg/kg/day (about 34 times an oral human dose of 40 mg on a body surface area basis).

A pre- and postnatal development study in rats with esomeprazole strontium (using equimolar doses compared to esomeprazole magnesium study) produced similar results in dams and pups as described above.

A follow-up developmental toxicity study in rats with further time points to evaluate pup bone development from postnatal day 2 to adulthood was performed with esomeprazole magnesium at oral doses of 280 mg/kg/day (about 68 times an oral human dose of 40 mg on a body surface area basis) where esomeprazole administration was from either gestational Day 7 or gestational Day 16 until parturition. When maternal administration was confined to gestation only, there were no effects on bone physeal morphology in the offspring at any age.

8.2 Lactation

Risk Summary

Available data from the published literature suggest both components of ZEGERID, omeprazole and sodium bicarbonate, are present in human milk. There are no clinical data on the effects of omeprazole or sodium bicarbonate on the breastfed infant or on milk production. The developmental and health benefits of breastfeeding should be considered along with the mother's clinical need for ZEGERID and any potential adverse effects on the breastfed infant from ZEGERID or from the underlying maternal condition.

8.4 Pediatric Use

Safety and effectiveness of ZEGERID have not been established in pediatric patients.

Juvenile Animal Data

Esomeprazole, an enantiomer of omeprazole, was shown to decrease body weight, body weight gain, femur weight, femur length, and overall growth at oral doses about 34 to 68 times a daily human dose of 40 mg esomeprazole or 40 mg omeprazole based on body surface area in a juvenile rat toxicity study. The animal to human dose multiples are based on the assumption of equal systemic exposure to esomeprazole in humans following oral administration of either 40 mg esomeprazole or 40 mg omeprazole.

A 28-day toxicity study with a 14-day recovery phase was conducted in juvenile rats with esomeprazole magnesium at doses of 70 to 280 mg/kg/day (about 17 to 68 times a daily oral human dose of 40 mg esomeprazole or 40 mg omeprazole on a body surface area basis). An increase in the number of deaths at the high dose of 280 mg/kg/day was observed when juvenile rats were administered esomeprazole magnesium from postnatal day 7 through postnatal day 35. In addition, doses equal to or greater than 140 mg/kg/day (about 34 times a daily oral human dose of 40 mg esomeprazole or 40 mg omeprazole on a body surface area basis), produced treatment-related decreases in body weight (approximately 14%) and body weight gain, decreases in femur weight and femur length, and affected overall growth. Comparable findings described above have also been observed in this study with another esomeprazole salt, esomeprazole strontium, at equimolar doses of esomeprazole.

8.5 Geriatric Use

Omeprazole was administered to over 2,000 elderly individuals (≥65 years of age) in clinical trials in the U.S. and Europe. There were no differences in safety and effectiveness between the elderly and younger subjects. Other reported clinical experience has not identified differences in response between the elderly and younger subjects, but greater sensitivity of some older individuals cannot be ruled out.

Pharmacokinetic studies with buffered omeprazole have shown the elimination rate was somewhat decreased in the elderly and bioavailability was increased. The plasma clearance of omeprazole was 250 mL/min (about half that of young subjects). The plasma half-life averaged one hour, about twice that in nonelderly, healthy subjects taking ZEGERID. However, no dosage adjustment is necessary in the elderly [see Clinical Pharmacology (12.3)].

8.6 Hepatic Impairment

In patients with hepatic impairment (Child-Pugh Class A, B, or C) exposure to omeprazole substantially increased compared to healthy subjects. Avoid use of ZEGERID in patients with hepatic impairment for maintenance of healing of erosive esophagitis [see Clinical Pharmacology (12.3)].

8.7 Asian Population

In studies of healthy subjects, Asians had approximately a four-fold higher exposure than Caucasians. Avoid use of ZEGERID in Asian patients for maintenance of healing of erosive esophagitis [see Clinical Pharmacology (12.5)].

10 OVERDOSAGE

If over-exposure occurs, call your Poison Control Center at 1-800-222-1222 for current information on the management of poisoning or overdosage.

Omeprazole

Reports have been received of overdosage with omeprazole in humans. Doses ranged up to 2,400 mg (120 times the usual recommended clinical dose). Manifestations were variable, but included confusion, drowsiness, blurred vision, tachycardia, nausea, vomiting, diaphoresis, flushing, headache, dry mouth, and other adverse reactions similar to those seen in clinical experience with the recommended dosage [see Adverse Reactions (6)]. Symptoms were transient, and no serious clinical outcome has been reported when omeprazole was taken alone. No specific antidote for omeprazole overdosage is known. Omeprazole is extensively protein bound and is, therefore, not readily dialyzable. In the event of overdosage, treatment should be symptomatic and supportive.

Sodium Bicarbonate

Overdosage of sodium bicarbonate can cause electrolyte abnormalities (hypocalcemia, hypokalemia, hypernatremia), metabolic alkalosis, and seizures. Institute supportive care and correct electrolyte abnormalities.

11 DESCRIPTION

ZEGERID (omeprazole and sodium bicarbonate) is a combination of omeprazole, a proton-pump inhibitor, and sodium bicarbonate, an antacid. Omeprazole is a substituted benzimidazole, 5-methoxy-2-[[(4-methoxy-3,5-dimethyl-2-pyridinyl)methyl]sulfinyl]-1H-benzimidazole, a racemic mixture of two enantiomers that inhibits gastric acid secretion. Its empirical formula is C17H19N3O3S, with a molecular weight of 345.42. The structural formula is:

Omeprazole is a white to off-white crystalline powder which melts with decomposition at about 155°C. It is a weak base, freely soluble in ethanol and methanol, slightly soluble in acetone and isopropanol and very slightly soluble in water. The stability of omeprazole is a function of pH; it is rapidly degraded in acid media but has acceptable stability under alkaline conditions.

ZEGERID is supplied as immediate-release capsules and unit-dose packets as powder for oral suspension. Each capsule contains either 40 mg or 20 mg of omeprazole and 1,100 mg of sodium bicarbonate with the following excipients: croscarmellose sodium and sodium stearyl fumarate. Packets of powder for oral suspension contain either 40 mg or 20 mg of omeprazole and 1,680 mg of sodium bicarbonate with the following excipients: sucralose, sucrose, xanthan gum, xylitol, and flavorings.

ZEGERID capsules and ZEGERID for oral suspension are immediate-release formulations that contain sodium bicarbonate which raises the gastric pH and thus protects omeprazole from acid degradation.

12 CLINICAL PHARMACOLOGY

12.1 Mechanism of Action

Omeprazole belongs to a class of antisecretory compounds, the substituted benzimidazoles, that suppress gastric acid secretion by specific inhibition of the H+/K+ ATPase enzyme system at the secretory surface of the gastric parietal cell. Because this enzyme system is regarded as the acid (proton) pump within the gastric mucosa, omeprazole has been characterized as a gastric acid-pump inhibitor, in that it blocks the final step of acid production. This effect is dose related and leads to inhibition of both basal and stimulated acid secretion irrespective of the stimulus.

12.2 Pharmacodynamics

Antisecretory Activity

Results from a pharmacokinetic/pharmacodynamic (PK/PD) study of the antisecretory effect of repeated once-daily dosing of 40 mg and 20 mg of ZEGERID for oral suspension in healthy subjects are shown in Table 8 below.

Table 8: Effect of ZEGERID for Oral Suspension on Intragastric pH, Day 7
 | Once-Daily Dosage of ZEGERID for Oral Suspension
Parameter | 40 mg omeprazole and; 1,680 mg sodium bicarbonate (n = 24) | 20 mg omeprazole and; 1,680 mg sodium bicarbonate (n = 28)
% Decrease from Baseline for Integrated Gastric Acidity (mmol•hr/L) | 84% | 82%
Coefficient of Variation | 20% | 24%
% Time Gastric pH > 4 [P < 0.05 20 mg vs. 40 mg] (Hours) | 77% (18.6 h) | 51% (12.2 h)
Coefficient of Variation | 27% | 43%
Median pH | 5.2 | 4.2
Coefficient of Variation | 17% | 37%
Note: Values represent medians. All parameters were measured over a 24-hour period.

Results from a separate PK/PD study of antisecretory effect on repeated once-daily dosing of 40 mg/1,100 mg and 20 mg/1,100 mg of ZEGERID capsules in healthy subjects show similar effects in general on the above three PD parameters as those for ZEGERID for oral suspension 40 mg/1,680 mg and 20 mg/1,680 mg, respectively.

The antisecretory effect lasts longer than would be expected from the very short (1 hour) plasma half-life, apparently due to irreversible binding to the parietal H+/K+ ATPase enzyme.

Enterochromaffin-like (ECL) Cell Effects

Human gastric biopsy specimens have been obtained from more than 3000 patients treated with omeprazole in long-term clinical trials. The incidence of ECL cell hyperplasia in these studies increased with time; however, no case of ECL cell carcinoids, dysplasia, or neoplasia has been found in these patients. These studies are of insufficient duration and size to rule out the possible influence of long-term administration of omeprazole on the development of any premalignant or malignant conditions.

Serum Gastrin Effects

In studies involving more than 200 patients, serum gastrin levels increased during the first 1 to 2 weeks of once-daily administration of therapeutic doses of omeprazole in parallel with inhibition of acid secretion. No further increase in serum gastrin occurred with continued treatment. In comparison with histamine H2-receptor antagonists, the median increases produced by 20 mg doses of omeprazole were higher (1.3 to 3.6-fold vs. 1.1- to 1.8-fold increase). Gastrin values returned to pretreatment levels, usually within 1 to 2 weeks after discontinuation of therapy.

Increased gastrin causes enterochromaffin-like cell hyperplasia and increased serum Chromogranin A (CgA) levels. The increased CgA levels may cause false positive results in diagnostic investigations for neuroendocrine tumors
[see Warnings and Precautions (5.12)].

Other Effects

Systemic effects of omeprazole in the central nervous system (CNS), cardiovascular and respiratory systems have not been found to date. Omeprazole, given in oral doses of 30 or 40 mg for 2 to 4 weeks, had no effect on thyroid function, carbohydrate metabolism, or circulating levels of parathyroid hormone, cortisol, estradiol, testosterone, prolactin, cholecystokinin or secretin.

No effect on gastric emptying of the solid and liquid components of a test meal was demonstrated after a single dose of omeprazole 90 mg. In healthy subjects, a single intravenous dose of omeprazole (0.35 mg/kg) had no effect on intrinsic factor secretion. No systematic dose-dependent effect has been observed on basal or stimulated pepsin output in humans. However, when intragastric pH is maintained at 4.0 or above, basal pepsin output is low, and pepsin activity is decreased.

As do other agents that elevate intragastric pH, omeprazole administered for 14 days in healthy subjects produced a significant increase in the intragastric concentrations of viable bacteria. The pattern of the bacterial species was unchanged from that commonly found in saliva. All changes resolved within three days of stopping treatment.

The course of Barrett’s esophagus in 106 patients was evaluated in a U.S. double-blind controlled study of omeprazole 40 mg twice daily for 12 months followed by 20 mg twice daily for 12 months or ranitidine 300 mg twice daily for 24 months. No clinically significant impact on Barrett’s mucosa by antisecretory therapy was observed. Although neosquamous epithelium developed during antisecretory therapy, complete elimination of Barrett’s mucosa was not achieved. No significant difference was observed between treatment groups in development of dysplasia in Barrett’s mucosa, and no patient developed esophageal carcinoma during treatment. No significant differences between treatment groups were observed in development of ECL cell hyperplasia, corpus atrophic gastritis, corpus intestinal metaplasia, or colon polyps exceeding 3 mm in diameter.

12.3 Pharmacokinetics

Absorption

Tables 9 and 10 show the systemic exposures and the time reach peak concentration (Tmax) of omeprazole in healthy subjects following administration of ZEGERID capsules and oral suspension, respectively, on an empty stomach one hour prior to a meal.

Table 9: Arithmetic Mean (CV%) of the Systemic Exposures (Cmax, AUC) and Tmax of Omeprazole after a Single Oral Dose and Multiple Once-Daily Doses of ZEGERID Capsules
 | 20 mg ZEGERID capsules |  |  | 40 mg ZEGERID capsules
 | Day 1 | Day 7 | % Change (Day 7/Day 1) | Day 1 | Day 7 | % Change (Day 7/Day 1)
Cmax (ng/mL) | 498.1 (50.9) | 679.8 (44.0) | 36 | 1154 (53.0) | 1526 (48.7) | 32
Tmax (hr); [min – max] | 0.61; [0.25-1.5] | 0.82; [0.25-1.5] | n.a. | 0.56; [0.25-1.5] | 0.97; [0.25-3.5] | n.a.
AUC0-inf [AUC0-24h was used on Day 7] (ng•hr/mL) | 509.7 (60.5) | 1029 (67.9) | 102 | 1882 (120) | 3866 (83.3) | 105
n.a.: not applicable

Table 10: Arithmetic Mean (CV%) of the Systemic Exposures (Cmax, AUC) and Tmax of Omeprazole after a Single Oral Dose and Multiple Once-Daily Doses of ZEGERID Oral Suspension
 | 20 mg ZEGERID oral suspension |  |  | 40 mg ZEGERID oral suspension
 | Day 1 | Day 7 | % Change; (Day 7/Day 1) | Day 1 | Day 7 | % Change (Day 7/Day 1)
Cmax (ng/mL) | 671.9 (43.8) | 902.2 (39.6) | 34 | 1412 (43.7) | 1954 (33.5) | 38
Tmax (hr); [min – max] | 0.50; [0.17-1.5] | 0.47; [0.17-1.0] | n.a. | 0.44; [0.17-1.0] | 0.58; [0.25-1.0] | n.a.
AUC0-inf [AUC0-24h was used on Day 7] (ng•hr/mL) | 825.4 (71.9) | 1449 (61.7) | 76 | 2228 (107) | 4692 (60.5) | 111
n.a.: not applicable

Following single or repeated once-daily dosing, peak plasma concentrations (Cmax) of omeprazole from ZEGERID were approximately proportional from 20 to 40 mg doses. A greater than dose proportional increase in mean steady-state AUC (more than three-fold increase on Day 7) was observed when doubling the dose to 40 mg. The bioavailability of omeprazole from ZEGERID increases upon repeated administration. The percent changes in Cmax and AUC between steady-state (Day 7) and single dose (Day 1) indicate omeprazole is a time-dependent autoinhibitor of CYP2C19.

When ZEGERID for oral suspension 40 mg was administered in a two-dose loading regimen, the omeprazole AUC(0-inf) (ng•hr/mL) was 1665 after Dose 1 and 3356 after Dose 2, while Tmax was approximately 30 minutes for both Dose 1 and Dose 2.

When ZEGERID for oral suspension 40 mg or ZEGERID capsule 40 mg is administered one hour after a meal, the omeprazole AUC is reduced by approximately 27% and 22%, respectively, relative to administration one hour prior to a meal [see Dosage and Administration (2.3)].

Distribution

Omeprazole is bound to plasma proteins. Protein binding is approximately 95%.

Elimination

Metabolism

Omeprazole is extensively metabolized by the cytochrome P450 (CYP) enzyme system. The major part of its metabolism is dependent on the polymorphically expressed CYP2C19 [see Clinical Pharmacology (12.5)], responsible for the formation of hydroxyomeprazole, the major metabolite in plasma. The remaining part is dependent on another specific isoform, CYP3A4, responsible for the formation of omeprazole sulphone.

The mean plasma omeprazole half-life following administration of ZEGERID capsule or ZEGERID oral suspension in healthy subjects is approximately 1 hour (range 0.4 to 4.2 hours), and the total body clearance is 500 to 600 mL/min.

Excretion

Following single-dose oral administration of a buffered solution of omeprazole, the majority of the dose (about 77%) is eliminated in urine as at least six metabolites. Two metabolites have been identified as hydroxyomeprazole and the corresponding carboxylic acid. The remainder of the dose was recoverable in feces. This implies a significant biliary excretion of the metabolites of omeprazole. Three metabolites have been identified in plasma – the sulfide and sulfone derivatives of omeprazole, and hydroxyomeprazole. These metabolites have very little or no antisecretory activity.

Specific Populations

Geriatric Patients

The elimination rate of omeprazole was somewhat decreased in the elderly, and bioavailability was increased. Omeprazole was 76% bioavailable when a single 40 mg oral dose of omeprazole (buffered solution) was administered to healthy elderly subjects versus 58% in young subjects given the same dose. Nearly 70% of the dose was recovered in urine as metabolites of omeprazole, and no unchanged drug was detected. The plasma clearance of omeprazole was 250 mL/min (about half that of young subjects), and its plasma half-life averaged one hour, similar to that of young healthy subjects.

Male and Female Patients

There are no known differences in the absorption or excretion of omeprazole between males and females.

Racial or Ethnic Groups

[see Clinical Pharmacology (12.5)]

Patients with Renal Impairment

In patients with chronic renal impairment (creatinine clearance between 10 and 62 mL/min/1.73 m^2), the disposition of omeprazole was very similar to that in healthy subjects, although there was a slight increase in bioavailability. Because urinary excretion is a primary route of excretion of omeprazole metabolites, their elimination slowed in proportion to the decreased creatinine clearance. This increase in bioavailability is not considered to be clinically meaningful.

Patients with Hepatic Impairment

In patients with chronic hepatic disease classified as Child-Pugh Class A (n=3), B (n=4) and C (n=1), the bioavailability of omeprazole increased to approximately 100% compared to healthy subjects, reflecting decreased first-pass effect, and the plasma half-life of the drug increased to nearly 3 hours compared to the in healthy subjects of 0.5 to 1 hour. Plasma clearance averaged 70 mL/min, compared to a value of 500 to 600 mL/min in healthy subjects [see Use in Specific Populations (8.6)].

Drug Interactions Studies

Effect of Omeprazole on Other Drugs

Omeprazole is a time-dependent inhibitor of CYP2C19 and can increase the systemic exposure of co-administered drugs that are CYP2C19 substrates. In addition, administration of omeprazole increases intragastric pH and can alter the systemic exposure of certain drugs that exhibit pH-dependent solubility [see Drug Interactions (7)].

Antiretrovirals

For some antiretroviral drugs, such as rilpivirine, atazanavir and nelfinavir, decreased serum concentrations have been reported when given together with omeprazole [see Drug Interactions (7)].

Rilpivirine: Following multiple doses of rilpivirine (150 mg, daily) and omeprazole (20 mg, daily), AUC was decreased by 40%, Cmax by 40%, and Cmin by 33% for rilpivirine.

Nelfinavir: Following multiple doses of nelfinavir (1250 mg, twice daily) and omeprazole (40 mg daily), AUC was decreased by 36% and 92%, Cmax by 37% and 89% and Cmin by 39% and 75% respectively for nelfinavir and M8.

Atazanavir: Following multiple doses of atazanavir (400 mg, daily) and omeprazole (40 mg, daily, 2 hours before atazanavir), AUC was decreased by 94%, Cmax by 96%, and Cmin by 95%.

Saquinavir: Following multiple dosing of saquinavir/ritonavir (1000/100 mg) twice daily for 15 days with omeprazole 40 mg daily co-administered days 11 to 15.

AUC was increased by 82%, Cmax by 75%, and Cmin by 106%. The mechanism behind this interaction is not fully elucidated. Therefore, clinical and laboratory monitoring for saquinavir toxicity is recommended during concurrent use with PRILOSEC.

Clopidogrel

In a crossover clinical study, 72 healthy subjects were administered clopidogrel (300 mg loading dose followed by 75 mg per day) alone and with omeprazole (80 mg at the same time as clopidogrel) for 5 days. The exposure to the active metabolite of clopidogrel was decreased by 46% (Day 1) and 42% (Day 5) when clopidogrel and omeprazole were administered together.

Results from another crossover study in healthy subjects showed a similar pharmacokinetic interaction between clopidogrel (300 mg loading dose/75 mg daily maintenance dose) and omeprazole 80 mg daily when coadministered for 30 days. Exposure to the active metabolite of clopidogrel was reduced by 41% to 46% over this time period.

In another study, 72 healthy subjects were given the same doses of clopidogrel and 80 mg omeprazole, but the drugs were administered 12 hours apart; the results were similar, indicating that administering clopidogrel and omeprazole at different times does not prevent their interaction [see Warnings and Precautions (5.8) and Drug Interactions (7)].

Mycophenolate Mofetil

Administration of omeprazole 20 mg twice daily for 4 days and a single 1000 mg dose of MMF approximately one hour after the last dose of omeprazole to 12 healthy subjects in a crossover study resulted in a 52% reduction in the Cmax and 23% reduction in the AUC of MPA [see Drug Interactions (7)].

Cilostazol

Omeprazole acts as an inhibitor of CYP2C19. Omeprazole, given in doses of 40 mg daily for one week to 20 healthy subjects in crossover study, increased Cmax and AUC of cilostazol by 18% and 26% respectively. The Cmax and AUC of one of the active metabolites, 3,4-dihydro-cilostazol, which has 4 to 7 times the activity of cilostazol, were increased by 29% and 69%, respectively. Co-administration of cilostazol with omeprazole is expected to increase concentrations of cilostazol and the above mentioned active metabolite [see Drug Interactions (7)].

Diazepam

Concomitant administration of omeprazole 20 mg once daily and diazepam 0.1 mg/kg given intravenously resulted in 27% decrease in clearance and 36% increase in diazepam half-life [see Drug Interactions (7)].

Digoxin

Concomitant administration of omeprazole 20 mg once daily and digoxin in healthy subjects increased the bioavailability of digoxin by 10% (30% in two subjects) [see Drug Interactions (7)].

Effect of Other Drugs on Omeprazole

Voriconazole

Concomitant administration of omeprazole and voriconazole (a combined inhibitor of CYP2C19 and CYP3A4) resulted in more than doubling of the omeprazole exposure. When voriconazole (400 mg every 12 hours for one day, followed by 200 mg once daily for 6 days) was given with omeprazole (40 mg once daily for 7 days) to healthy subjects, the steady-state Cmax and AUC0-24 of omeprazole significantly increased: an average of 2 times (90% CI: 1.8, 2.6) and 4 times (90%

CI: 3.3, 4.4), respectively, as compared to when omeprazole was given without voriconazole [see Drug Interactions (7)].

12.5 Pharmacogenomics

CYP2C19, a polymorphic enzyme, is involved in the metabolism of omeprazole. The CYP2C19*1 allele is fully functional while the CYP2C19*2 and *3 alleles are nonfunctional. There are other alleles associated with no or reduced enzymatic function. Patients carrying two fully functional alleles are extensive metabolizers and those carrying two loss-of-function alleles are poor metabolizers. In extensive metabolizers, omeprazole is primarily metabolized by CYP2C19.

The systemic exposure to omeprazole varies with a patient’s metabolism status: poor metabolizers > intermediate

metabolizers > extensive metabolizers. Approximately 3% of Caucasians and 15 to 20% of Asians are CYP2C19 poor metabolizers.

In pharmacokinetic studies of single 20 mg omeprazole dose, the AUC of omeprazole in Asian subjects was approximately four-fold of that in Caucasians [see Use in Specific Populations (8.7)].

13 NONCLINICAL TOXICOLOGY

13.1 Carcinogenesis, Mutagenesis, Impairment of Fertility

In two 24-month carcinogenicity studies in rats, omeprazole at daily doses of 1.7, 3.4, 13.8, 44 and 140.8 mg/kg/day (approximately 0.4 to 34.2 times the human dose of 40 mg/day on a body surface area basis) produced gastric ECL cell carcinoids in a dose-related manner in both male and female rats; the incidence of this effect was markedly higher in female rats, which had higher blood levels of omeprazole. Gastric carcinoids seldom occur in the untreated rat. In addition, ECL cell hyperplasia was present in all treated groups of both sexes. In one of these studies, female rats were treated with 13.8 mg omeprazole/kg/day (approximately 3.36 times the human dose of 40 mg/day on a body surface area basis) for one year, then followed for an additional year without the drug. No carcinoids were seen in these rats. An increased incidence of treatment-related ECL cell hyperplasia was observed at the end of one year (94% treated versus 10% controls). By the second year the difference between treated and control rats was much smaller (46% versus 26%) but still showed more hyperplasia in the treated group. Gastric adenocarcinoma was seen in one rat (2%). No similar tumor was seen in male or female rats treated for two years. For this strain of rat no similar tumor has been noted historically, but a finding involving only one tumor is difficult to interpret. In a 52-week toxicity study in Sprague Dawley rats, brain astrocytomas were found in a small number of males that received omeprazole at dose levels of 0.4, 2, and 16 mg/kg/day (about 0.1 to 3.9 times the human dose of 40 mg/day on a body surface area basis). No astrocytomas were observed in female rats in this study. In a 2-year carcinogenicity study in Sprague Dawley rats, no astrocytomas were found in males and females at the high dose of 140.8 mg/kg/day (about 34 times the human dose of 40 mg/day on a body surface area basis). A 78-week mouse carcinogenicity study of omeprazole did not show increased tumor occurrence, but the study was not conclusive. A 26-week p53 (+/-) transgenic mouse carcinogenicity study was not positive.

Omeprazole was positive for clastogenic effects in an in vitro human lymphocyte chromosomal aberration assay, in one of two in vivo mouse micronucleus tests, and in an in vivo bone marrow cell chromosomal aberration assay. Omeprazole was negative in the in vitro Ames test, an in vitro mouse lymphoma cell forward mutation assay and an in vivo rat liver DNA damage assay.

In a 24-month carcinogenicity studies in rats, a dose-related significant increase in gastric carcinoid tumors and ECL cell hyperplasia was observed in both male and female animals. Carcinoid tumors have also been observed in rats subjected to fundectomy or long-term treatment with other PPIs or high doses of H2-receptor antagonists.

Omeprazole at oral doses up to 138 mg/kg/day (about 33.6 times the human dose of 40 mg/day on a body surface area basis) was found to have no effect on the fertility and general reproductive performance in rats.

14 CLINICAL STUDIES

The effectiveness of ZEGERID has been established, in part, based on studies of an oral delayed-release omeprazole product for the treatment of active duodenal ulcer, active benign gastric ulcer, symptomatic GERD, EE due to acid-mediated GERD, and maintenance of healing of EE due to acid-mediated GERD [see Clinical Studies (14.1, 14.2, 14.3, 14.4, 14.5)].

ZEGERID for oral suspension was studied for the reduction of risk of upper GI bleeding in critically ill adult patients [see Clinical Studies (14.6)].

14.1 Active Duodenal Ulcer

In a multicenter, double-blind, placebo-controlled study of 147 patients with endoscopically documented duodenal ulcer, the percentage of patients healed (per protocol) at 2 and 4 weeks was significantly higher with omeprazole delayed-release capsules 20 mg once a day than with placebo (p ≤ 0.01) (See Table 11).

Table 11: Treatment of Active Duodenal Ulcer
% of Patients Healed
 | Omeprazole 20 mg a.m. (n = 99) | Placebo a.m. (n = 48)
Week 2 | 41 [(p ≤ 0.01)] | 13
Week 4 | 75 | 27

Complete daytime and nighttime pain relief occurred significantly faster (p ≤ 0.01) in patients treated with omeprazole 20 mg than in patients treated with placebo. At the end of the study, significantly more patients who had received omeprazole had complete relief of daytime pain (p ≤ 0.05) and nighttime pain (p ≤ 0.01).

In a multicenter, double-blind study of 293 patients with endoscopically documented duodenal ulcer, the percentage of patients healed (per protocol) at 4 weeks was significantly higher with omeprazole 20 mg once a day than with ranitidine 150 mg twice daily (p < 0.01) (See Table 12).

Table 12: Treatment of Active Duodenal Ulcer % of Patients Healed
 | Omeprazole 20 mg a.m. (n = 145) | Ranitidine 150 mg twice daily (n = 148)
Week 2 | 42 | 34
Week 4 | 82 [(p < 0.01)] | 63

Healing occurred significantly faster in patients treated with omeprazole than in those treated with ranitidine 150 mg twice daily (p < 0.01).

In a foreign multinational randomized, double-blind study of 105 patients with endoscopically documented duodenal ulcer, 40 mg and 20 mg of omeprazole were compared to 150 mg twice daily of ranitidine at 2, 4 and 8 weeks. At 2 and 4 weeks both doses of omeprazole were statistically superior (per protocol) to ranitidine, but 40 mg was not superior to 20 mg of omeprazole, and at 8 weeks there was no significant difference between any of the active drugs. (See Table 13.)

Table 13: Treatment of Active Duodenal Ulcer % of Patients Healed
 | Omeprazole |  | Ranitidine 150 mg twice daily (n = 35)
 | 40 mg (n = 36) | 20 mg (n = 34) | Ranitidine 150 mg twice daily (n = 35)
Week 2 | 83 [(p≤0.01)] | 83 | 53
Week 4 | 100 | 97 | 82
Week 8 | 100 | 100 | 94

14.2 Active Benign Gastric Ulcer

In a U.S. multicenter, double-blind study of omeprazole 40 mg once a day, 20 mg once a day, and placebo in 520 patients with endoscopically diagnosed gastric ulcer, the following results were obtained. (See Table 14.)

Table 14: Treatment of Gastric Ulcer % of Patients Healed (All Patients Treated)
 | Omeprazole 40 mg once daily (n = 214) | Omeprazole 20 mg once daily (n = 202) | Placebo (n = 104)
Week 4 | 55.6 [(p < 0.01) omeprazole 40 mg or 20 mg versus placebo] | 47.5 | 30.8
Week 8 | 82.7 [(p < 0.05) omeprazole 40 mg versus 20 mg] | 74.8 | 48.1

For the stratified groups of patients with ulcer size less than or equal to 1 cm, no difference in healing rates between 40 mg and 20 mg was detected at either 4 or 8 weeks. For patients with ulcer size greater than 1 cm, 40 mg was significantly more effective than 20 mg at 8 weeks.

In a foreign, multinational, double-blind study of 602 patients with endoscopically diagnosed gastric ulcer, omeprazole 40 mg once a day, 20 mg once a day, and ranitidine 150 mg twice a day were evaluated. (See Table 15.)

Table 15: Treatment of Gastric Ulcer % of Patients Healed (All Patients Treated)
 | Omeprazole 40 mg once daily (n = 187) | Omeprazole 20 mg once daily (n = 200) | Ranitidine 150 mg twice daily (n = 199)
Week 4 | 78.1 [(p < 0.01) omeprazole 40 mg versus ranitidine] [(p < 0.01) omeprazole 40 mg versus 20 mg] | 63.5 | 56.3
Week 8 | 91.4 | 81.5 | 78.4

14.3 Symptomatic GERD

A placebo-controlled study was conducted in Scandinavia to compare the efficacy of omeprazole 20 mg or 10 mg once daily for up to 4 weeks in the treatment of heartburn and other symptoms in GERD patients without EE. Results are shown in Table 16.

Table 16: % Successful Symptomatic Outcome [Defined as complete resolution of heartburn]
 | Omeprazole 20 mg a.m. | Omeprazole 10 mg a.m. | Placebo a.m.
All Patients | 46 [(p < 0.005) versus 10 mg] [(p < 0.005) versus placebo] (n = 205) | 31 (n = 199) | 13 (n = 105)
Patients with Confirmed GERD | 56 (n = 115) | 36 (n = 109) | 14 (n = 59)

14.4 EE Due to Acid-Mediated GERD

In a U.S. multicenter, double-blind, placebo-controlled study of 40 mg or 20 mg of omeprazole delayed-release capsules in patients with symptoms of GERD and endoscopically diagnosed erosive esophagitis of grade 2 or above, the percentage healing rates (per protocol) were as shown in Table 17.

Table 17: % Patients Healed
 | Omeprazole 40 mg (n = 87) | Omeprazole 20 mg (n = 83) | Placebo (n = 43)
Week 4 | 45 [(p < 0.01) omeprazole versus placebo.] | 39 | 7
Week 8 | 75 | 74 | 14

In this study, the 40 mg dose was not superior to the 20 mg dose of omeprazole in the percentage healing rate. Other controlled clinical trials have also shown that omeprazole is effective in severe GERD. In comparisons with histamine H2‑receptor antagonists in patients with erosive esophagitis, grade 2 or above, omeprazole in a dose of 20 mg was significantly more effective than the active controls. Complete daytime and nighttime heartburn relief occurred significantly faster (p < 0.01) in patients treated with omeprazole than in those taking placebo or histamine H2-receptor antagonists.

In this and five other controlled GERD studies, significantly more patients taking 20 mg omeprazole (84%) reported complete relief of GERD symptoms than patients receiving placebo (12%).

14.5 Maintenance of Healing of EE Due to Acid-Mediated GERD

In a U.S. double-blind, randomized, multicenter, placebo-controlled study; two dose regimens of omeprazole were studied in patients with endoscopically confirmed healed esophagitis. Results to determine maintenance of healing of erosive esophagitis are shown in Table 18.

Table 18: Life Table Analysis
 | Omeprazole 20 mg once daily (n = 138) | Omeprazole 20 mg 3 days per week (n = 137) | Placebo (n = 131)
Percent in Endoscopic Remission at 6 Months | 70 [(p < 0.01) omeprazole 20 mg once daily versus omeprazole 20 mg 3 consecutive days per week or placebo.] | 34 | 11

In an international, multicenter, double-blind study, omeprazole 20 mg daily and 10 mg daily were compared to ranitidine 150 mg twice daily in patients with endoscopically confirmed healed esophagitis. Table 19 provides the results of this study for maintenance of healing of EE.

Table 19: Life Table Analysis
 | Omeprazole 20 mg once daily (n = 131) | Omeprazole 10 mg once daily (n = 133) | Ranitidine 150 mg twice daily (n = 128)
Percent in Endoscopic Remission at 12 Months | 77 [(p = 0.01) omeprazole 20 mg once daily versus omeprazole 10 mg once daily or Ranitidine.] | 58 [(p = 0.03) omeprazole 10 mg once daily versus Ranitidine.] | 46

In patients who initially had grades 3 or 4 erosive esophagitis, for maintenance after healing 20 mg daily of omeprazole was effective, while 10 mg did not demonstrate effectiveness.

14.6 Reduction of Risk of Upper Gastrointestinal Bleeding in Critically Ill Patients

A double-blind, multicenter, randomized, non-inferiority clinical trial was conducted to compare ZEGERID oral suspension and intravenous cimetidine for the reduction of risk of upper gastrointestinal (GI) bleeding in critically ill patients (mean APACHE II score = 23.7). The primary endpoint was significant upper GI bleeding defined as bright red blood which did not clear after adjustment of the nasogastric tube and a 5 to 10 minute lavage, or persistent Gastroccult-positive coffee grounds for 8 consecutive hours which did not clear with 100 mL lavage. ZEGERID oral suspension was administered as 40 mg (two doses administered 6 to 8 hours apart on the first day via orogastric or nasogastric tube, followed by 40 mg once daily thereafter) and intravenous cimetidine (300 mg bolus, followed by 50 to 100 mg/hr continuously thereafter) for up to 14 days (mean = 6.8 days). A total of 359 patients were studied, age range 16 to 91 (mean = 56 years), 58.5% were males, and 64% were Caucasians. The results of the study showed that ZEGERID oral suspension was non-inferior to intravenous cimetidine, 7/178 (3.9%) patients in the ZEGERID group vs. 10/181 (5.5%) patients in the cimetidine group experienced clinically significant upper GI bleeding.

16 HOW SUPPLIED/STORAGE AND HANDLING

ZEGERID is supplied as:

ZEGERID Capsules
NDC | Strength | Quantity | Description
68012‑102‑30 | 20 mg omeprazole and 1,100 mg sodium bicarbonate | Bottles of 30 capsules | Opaque, hard gelatin, white capsule, imprinted with the Santarus logo and “20”
68012‑104‑30 | 40 mg omeprazole and 1,100 mg sodium bicarbonate | Bottles of 30 capsules | Opaque, hard gelatin, colored dark blue and white capsule, imprinted with the Santarus logo and “40”
ZEGERID for Oral Suspension
NDC | Strength | Quantity | Description
68012‑052‑30 | 20 mg omeprazole and 1,680 mg sodium bicarbonate | Cartons of 30 unit‑dose packets | White, flavored powder packaged in unit-dose packets
68012‑054‑30 | 40 mg omeprazole and 1,680 mg sodium bicarbonate | Cartons of 30 unit‑dose packets | White, flavored powder packaged in unit-dose packets.

Storage

Store at 20° to 25°C (68° to 77°F); excursions permitted to 15° to 30°C (59° to 86°F) [see USP Controlled Room Temperature].

Keep container tightly closed. Protect from light and moisture.

17 PATIENT COUNSELING INFORMATION

Advise the patient to read the FDA-approved patient labeling (Medication Guide).

Acute Tubulointerstitial Nephritis

Advise the patient to call their healthcare provider immediately if they experience signs and/or symptoms associated with acute tubulointerstitial nephritis [see Warnings and Precautions (5.2)].

Sodium Bicarbonate Buffer Content

Inform patients on a sodium-restricted diet or patients at risk of developing congestive heart failure of the sodium content of ZEGERID capsules (304 mg per capsule) and ZEGERID for oral suspension (460 mg per packet).

Advise patients that:

- chronic use of bicarbonate with calcium or milk can cause milk-alkali syndrome
- chronic use of sodium bicarbonate may systemic alkalosis
- increased sodium intake can cause swelling and weight gain.

If any of these occur, instruct patients to contact their healthcare provider [see Warnings and Precautions (5.3)].

Clostridium difficile-Associated Diarrhea

Advise the patient to immediately call their healthcare provider if they experience diarrhea that does not improve [see Warnings and Precautions (5.4)].

Bone Fracture

Advise the patient to report any fractures, especially of the hip, wrist or spine, to their healthcare provider [see Warnings and Precautions (5.5)].

Severe Cutaneous Adverse Reactions

Advise the patient to discontinue ZEGERID and immediately call their healthcare provider at first appearance of a severe cutaneous adverse reaction or other sign of hypersensitivity [see Warnings and Precautions (5.6)].

Cutaneous and Systemic Lupus Erythematosus

Advise the patient to immediately call their healthcare provider for any new or worsening of symptoms associated with cutaneous or systemic lupus erythematosus [see Warnings and Precautions (5.7)].

Cyanocobalamin (Vitamin B-12) Deficiency

Advise the patient to report any clinical symptoms that may be associated with cyanocobalamin deficiency to their healthcare provider if they have been receiving ZEGERID for longer than 3 years [see Warnings and Precautions (5.9)].

Hypomagnesemia and Mineral Metabolism

Advise the patient to report any clinical symptoms that may be associated with hypomagnesemia, hypocalcemia, and/or hypokalemia to their healthcare provider, if they have been receiving ZEGERID for at least 3 months [see Warnings and Precautions (5.10)].

Drug Interactions

Advise patients to report to their healthcare provider if they start treatment with rilpivirine-containing products, clopidogrel, St. John’s wort or rifampin, or if they take high-dose methotrexate [see Contraindications (4) and Warnings and Precautions (5.8, 5.11, 5.13)].

Administration

Instruct patients not to substitute:

- Two packets of 20 mg ZEGERID for oral suspension with one packet of 40 mg ZEGERID for oral suspension.
- Two 20 mg ZEGERID capsules with one 40 mg ZEGERID capsule.

Administration of ZEGERID Capsules

- Instruct patients to swallow ZEGERID capsules intact with water. Do not open the capsule and do not administer with liquids other than water.
- Instruct patients to take ZEGERID capsules on an empty stomach at least one hour before a meal [see Dosage and Administration (2.3)].

Administration of ZEGERID for Oral Suspension

- Advise patients that ZEGERID for oral suspension is intended to be mixed with water and administered orally or via a nasogastric (NG)/orogastric (OG) tube, as described in the Medication Guide.
- Instruct patients to suspend enteral feeding approximately 3 hours before and 1 hour after administration of ZEGERID for oral suspension [see Dosage and Administration (2.3)].

Distributed by:
Salix Pharmaceuticals, a division of
Bausch Health US, LLC
Bridgewater, NJ 08807 USA
ZEGERID is a trademark of Salix Pharmaceuticals, Inc. or its affiliates.
Any other product/brand names are trademarks of the respective owners.
© 2023 Salix Pharmaceuticals, Inc. or its affiliates
9658604

MEDICATION GUIDE

ZEGERID® (ze-ger-id)

(omeprazole and sodium bicarbonate)

for oral suspension and capsules, for oral use

What is the most important information I should know about ZEGERID?

ZEGERID may help your acid-related symptoms, but you could still have serious stomach problems. Talk with your doctor.

ZEGERID can cause serious side effects, including:

- A type of kidney problem (acute tubulointerstitial nephritis). Some people who take proton pump inhibitor (PPI) medicines, including ZEGERID, may develop a kidney problem called acute tubulointerstitial nephritis that can happen at any time during treatment with ZEGERID. Call your doctor right away if you have a decrease in the amount that you urinate or if you have blood in your urine.
- ZEGERID contains sodium bicarbonate. Long-term use of bicarbonate with calcium or milk can cause a condition called “milk-alkali syndrome”. Long-term use of sodium bicarbonate can cause a condition called “systemic alkalosis”. Talk to your doctor about any questions you may have. Too much sodium can cause swelling and weight gain. Tell your doctor if you are on a low-sodium diet or if you have Bartter’s Syndrome (a rare kidney disorder). Tell your doctor right away if you have confusion, shaking hands, dizziness, muscle twitching, nausea, vomiting, and numbness or tingling in the face, arms, or legs.
- Diarrhea caused by an infection (Clostridium difficile) in your intestines. Call your doctor right away if you have watery stools or stomach pain that does not go away. You may or may not have a fever.
- Bone fractures (hip, wrist, or spine). Bone fractures in the hip, wrist or spine may happen in people who take multiple daily doses of PPI medicines and for a long period of time (a year or longer). Tell your doctor if you have bone fracture, especially in the hip, wrist, or spine. Certain types of lupus erythematosus. Lupus erythematosus is an autoimmune disorder (the body’s immune cells attack other cells or organs in the body). Some people who take PPI medicines, including ZEGERID, may develop certain types of lupus erythematosus or have worsening of the lupus they already have. Call your doctor right away if you have new or worsening joint pain or a rash on your cheeks or arms that gets worse in the sun.

Talk to your doctor about your risk of these serious side effects.

ZEGERID can have other serious side effects. See “What are the possible side effects of ZEGERID?”

What is ZEGERID?

A prescription medicine called a proton pump inhibitor (PPI) used to reduce the amount of acid in your stomach.

ZEGERID for oral suspension and ZEGERID capsules is used in adults for:

- up to 8 weeks for the healing of duodenal ulcers.
- up to 8 weeks for the healing of stomach ulcers.
- up to 4 weeks to treat heartburn and other symptoms that happen with gastroesophageal reflux disease (GERD).
- up to 8 weeks for the healing and symptom relief of acid-related damage to the lining of the esophagus (called erosive esophagitis or EE). Your doctor may prescribe another 4 weeks of ZEGERID in patients whose EE does not heal.
- maintaining healing of EE and to help prevent the return of heartburn symptoms caused by GERD. It is not known if ZEGERID is safe and effective when used for longer than 12 months for this purpose.

ZEGERID for oral suspension is used:

- in critically ill adults to lower the risk of stomach bleeding (40 mg oral suspension only).

It is not known if ZEGERID is safe and effective in children.

Do not take ZEGERID if you are:

- allergic to omeprazole, any other PPI medicine, or any of the ingredients in ZEGERID. See the end of this Medication Guide for a complete list of ingredients in ZEGERID.
- taking a medicine that contains rilpivirine, used to treat HIV-1 (Human Immunodeficiency Virus).

Before taking ZEGERID, tell your doctor about all of your medical conditions, including if you:

- have low magnesium, calcium, or potassium levels in your blood.
- have problems with the acid-base (pH) balance in your body.
- have liver problems.
- have heart failure.
- are on a low-sodium diet.
- have Bartter’s syndrome (a rare kidney problem).
- are of Asian descent and have been told that your body’s ability to break down (metabolize) omeprazole is poor or if your genotype called CYP2C19 is not known.
- are pregnant or plan to become pregnant. It is not known if ZEGERID will harm your unborn baby.
- are breastfeeding or plan to breastfeed. ZEGERID can pass into your breast milk. Talk with your doctor about the best way to feed your baby if you take ZEGERID.

Tell your doctor about all the medicines you take, including prescription and over-the-counter medicines, vitamins and herbal supplements. Especially tell your doctor if you take:

- digoxin (Lanoxin)
- clopidogrel (Plavix)
- St. John’s wort (Hypericum perforatum)
- rifampin (Rifater, Rifamate, Rimactane, Rifadin)
- methotrexate

Ask your doctor or pharmacist for a list of these medicines, if you are not sure.

Know the medicines that you take. Keep a list of them to show your doctor and pharmacist when you get a new medicine.

How should I take ZEGERID?

- Take ZEGERID exactly as prescribed by your doctor.
- Do not change your dose or stop taking ZEGERID without talking to your doctor.
- Swallow ZEGERID capsules whole with water. Do not use other liquids. Do not crush or chew the capsule. Do not open the capsule and sprinkle contents into food.
- Take ZEGERID capsules on an empty stomach at least 1 hour before a meal.
- ZEGERID can be taken by mouth or given through a nasogastric (NG) or orogastric (OG) tube.
- See the “Instructions for Use” that come with ZEGERID for instructions on how to mix ZEGERID for oral suspension with water and give the medicine through a NG tube or OG tube.
- If you miss a dose of ZEGERID, take it as soon as you remember. If it is almost time for your next dose, do not take the missed dose. Take the next dose at your regular time. Do not take two doses to make up for a missed dose.
- Do not substitute two 20 mg packets for one 40 mg packet of ZEGERID for oral Suspension because you will receive twice the amount of sodium bicarbonate. Talk to your doctor if you have questions.
- Do not substitute two 20 mg capsules for one 40 mg capsule of ZEGERID because you will receive twice the amount of sodium bicarbonate. Talk to your doctor if you have questions.
- If you take too much ZEGERID, call your doctor or Poison Control Center at 1-800-222-1222 right away or go to the nearest hospital emergency room.

What are the possible side effects of ZEGERID?

ZEGERID can cause serious side effects, including:

- See “What is the most important information I should know about ZEGERID?”
- Low vitamin B-12 levels in your body can happen in people who have taken ZEGERID for a long time (more than 3 years). Tell your doctor if you have symptoms of low vitamin B-12 levels, including shortness of breath, lightheadedness, irregular heartbeat, muscle weakness, pale skin, feeling tired, mood changes, and tingling or numbness in the arms and legs.
- Low magnesium levels in your body can happen in people who have taken ZEGERID for at least 3 months. Tell your doctor right away if you have symptoms of low magnesium levels, including seizures, dizziness, irregular heartbeat, jitteriness, muscle aches or weakness, and spasms of hands, feet or voice.
- Stomach growths (fundic gland polyps). People who take PPI medicines for a long time have an increased risk of developing a certain type of stomach growths called fundic gland polyps, especially after taking PPI medicines for more than 1 year.
- Severe skin reactions. ZEGERID can cause rare but severe skin reactions that may affect any part of your body. These serious skin reactions may need to be treated in a hospital and may be life threatening:
- Skin rash which may have blistering, peeling or bleeding on any part of your skin (including your lips, eyes, mouth, nose, genitals, hands or feet).
- You may also have fever, chills, body aches, shortness of breath, or enlarged lymph nodes.
Stop taking ZEGERID and call your doctor right away. These symptoms may be the first sign of a severe skin reaction.
- The most common side effects of ZEGERID include:
- headache
- abdominal pain
- nausea
- diarrhea
- vomiting
- gas

These are not all the possible side effects of ZEGERID.

Call your doctor for medical advice about side effects. You may report side effects to FDA at 1-800-FDA-1088.

How should I store ZEGERID?

- Store ZEGERID at room temperature between 68°F to 77°F (20°C to 25°C).
- Keep ZEGERID in a tightly closed container.
- Keep ZEGERID in a dry place and out of light.

Keep ZEGERID and all medicines out of the reach of children.

General information about the safe and effective use of ZEGERID

Medicines are sometimes prescribed for purposes other than those listed in a Medication Guide. Do not use ZEGERID for any condition for which it was not prescribed. Do not give ZEGERID to other people, even if they have the same symptoms that you have. It may harm them.

You can also ask your doctor or pharmacist for information about ZEGERID that is written for health professionals.

What are the ingredients in ZEGERID?

Active ingredients: omeprazole and sodium bicarbonate

Inactive ingredients in ZEGERID for oral suspension: xylitol, sucrose, sucralose, xanthan gum, and flavorings.

Inactive ingredients in ZEGERID capsules, for oral use: croscarmellose sodium and sodium stearyl fumarate.

Distributed by:
Salix Pharmaceuticals, a division of
Bausch Health US, LLC
Bridgewater, NJ 08807 USA
ZEGERID is a trademark of Salix Pharmaceuticals, Inc. or its affiliates.
Any other product/brand names are trademarks of the respective owners.
© 2023 Salix Pharmaceuticals, Inc. or its affiliates
For more information, go to www.Salix.com or 1-800-321-4576.
This Medication Guide has been approved by the U.S. Food and Drug Administration.
Revised: 07/2023
9658604

INSTRUCTIONS FOR USE

ZEGERID® (ze-ger-id)

(omeprazole and sodium bicarbonate)

for oral suspension

Taking ZEGERID for oral suspension:

Important: ZEGERID should be taken on an empty stomach at least 1 hour before a meal.

1. ZEGERID comes in packets containing 20 mg or 40 mg of ZEGERID.
2. Use an oral syringe to draw up the amount of water needed to mix your dose. Ask your pharmacist for an oral syringe.
3. Using the oral syringe, draw up 5 mL to 10 mL of water and add the water to a small cup. Do not mix ZEGERID with foods or liquids other than water.
4. Empty the contents of the packet into the small cup.
5. Stir well to dissolve the powder and drink the mixture right away.
6. If any medicine remains after drinking, add more water, stir, and drink right away.

Giving ZEGERID for oral suspension with water through a nasogastric (NG) tube or orogastric (OG) tube:

Important: For patients receiving ZEGERID through a NG tube or OG tube, enteral feeding should be stopped approximately 3 hours before giving ZEGERID. You should wait at least 1 hour after giving ZEGERID before you start enteral feeding again.

1. ZEGERID comes in packets containing 20 mg or 40 mg of ZEGERID.
2. You will mix ZEGERID with 20 mL of water in a catheter tipped syringe.
3. Use only a catheter tipped syringe to give ZEGERID through the NG or OG tube. Talk to your doctor about the size catheter tipped syringe you should use.
4. Add 20 mL of water to the catheter tipped syringe. Do not use any food or liquids other than water to mix ZEGERID.
5. Add the contents of 1 packet of ZEGERID to the syringe.
6. Shake the syringe well to dissolve the powder.
7. Inject the medicine through the NG or OG tube into the stomach right away.
8. Refill the syringe with the same amount of water (20 mL) you used to prepare your dose of ZEGERID.
9. Shake the syringe and flush any remaining medicine from the NG tube or OG tube into the stomach.

Distributed by:
Salix Pharmaceuticals, a division of
Bausch Health US, LLC
Bridgewater, NJ 08807 USA
ZEGERID is a trademark of Salix Pharmaceuticals, Inc. or its affiliates.

Any other product/brand names are trademarks of the respective owners.

© 2023 Salix Pharmaceuticals, Inc. or its affiliates

9658604 Revised: 07/2023

PACKAGE/LABEL PRINCIPAL DISPLAY PANEL– 20mg sachet

NDC 68012-052-30

RX Only

Zegerid®

(omeprazole/sodium bicarbonate)

For Oral Suspension

Contains 30 single

20-mg dose packets

20 mg/1,680 mg

PHARMACIST: Dispense the enclosed

Medication Guide to each patient.

For more information, call 1-800-321-4576.

Salix PHARMACEUTICALS

PACKAGE/LABEL PRINCIPAL DISPLAY PANEL- 40 mg sachet

NDC 68012-054-30

RX Only

Zegerid®

(omeprazole/sodium bicarbonate)

For Oral Suspension

Contains 30 single

40-mg dose packets

40 mg/1,680 mg

PHARMACIST: Dispense the enclosed

Medication Guide to each patient.

For more information, call 1-800-321-4576.

Salix PHARMACEUTICALS

Package/Label Display Panel - 20 mg capsules

Rx only

NDC 68012-102-30

Zegerid®

(omeprazole/sodium bicarbonate)

Capsules

30 Capsules

20mg/1100mg

PHARMACIST: Dispense the enclosed

Medication Guide to each patient.

Package/Label Display Panel – 40 mg capsules

NDC 68012-104-30

Rx only

Zegerid®

(omeprazole/sodium bicarbonate)

Capsules

30 Capsules

40mg/1100mg

PHARMACIST: Dispense the enclosed

Medication Guide to each patient.